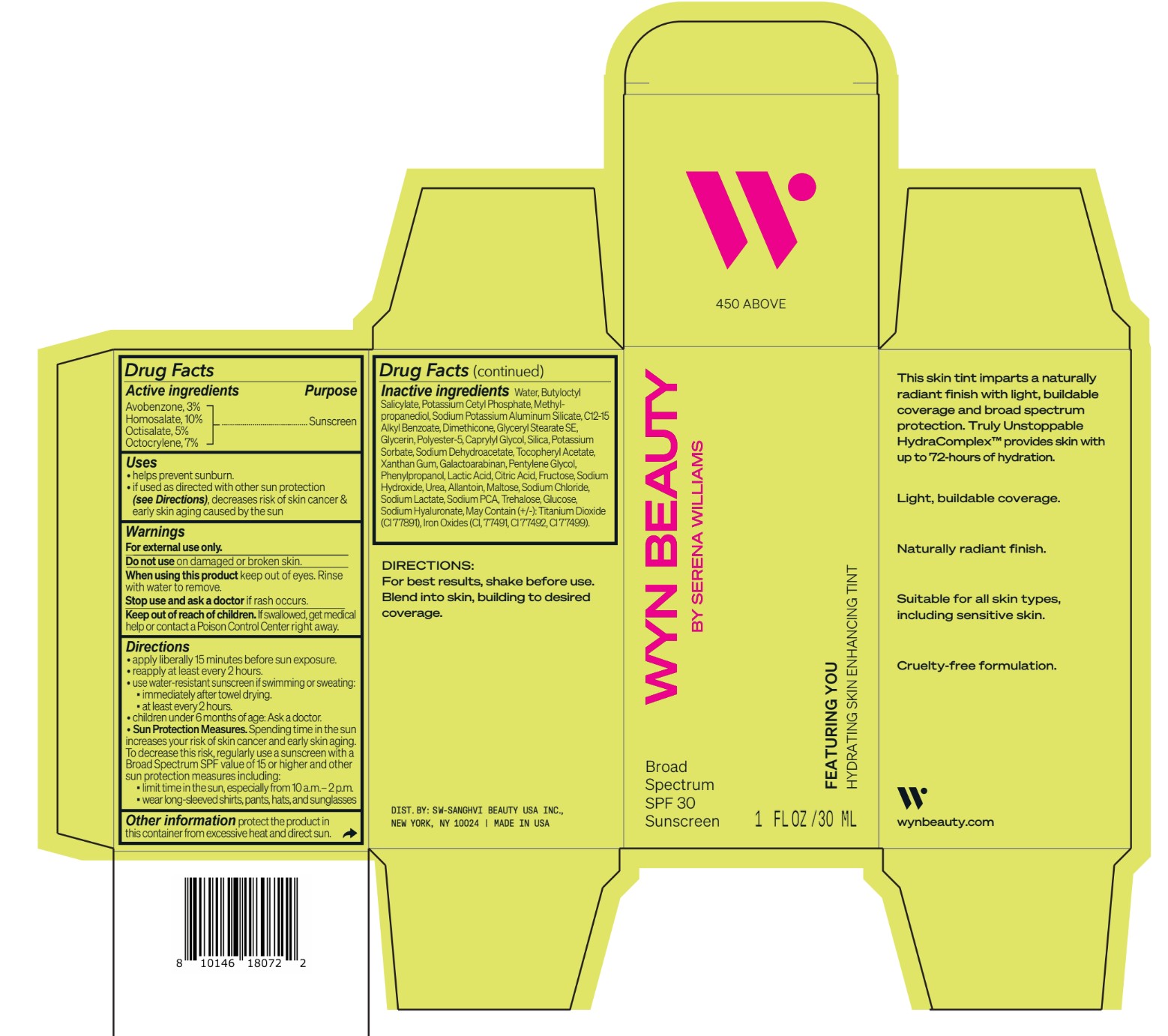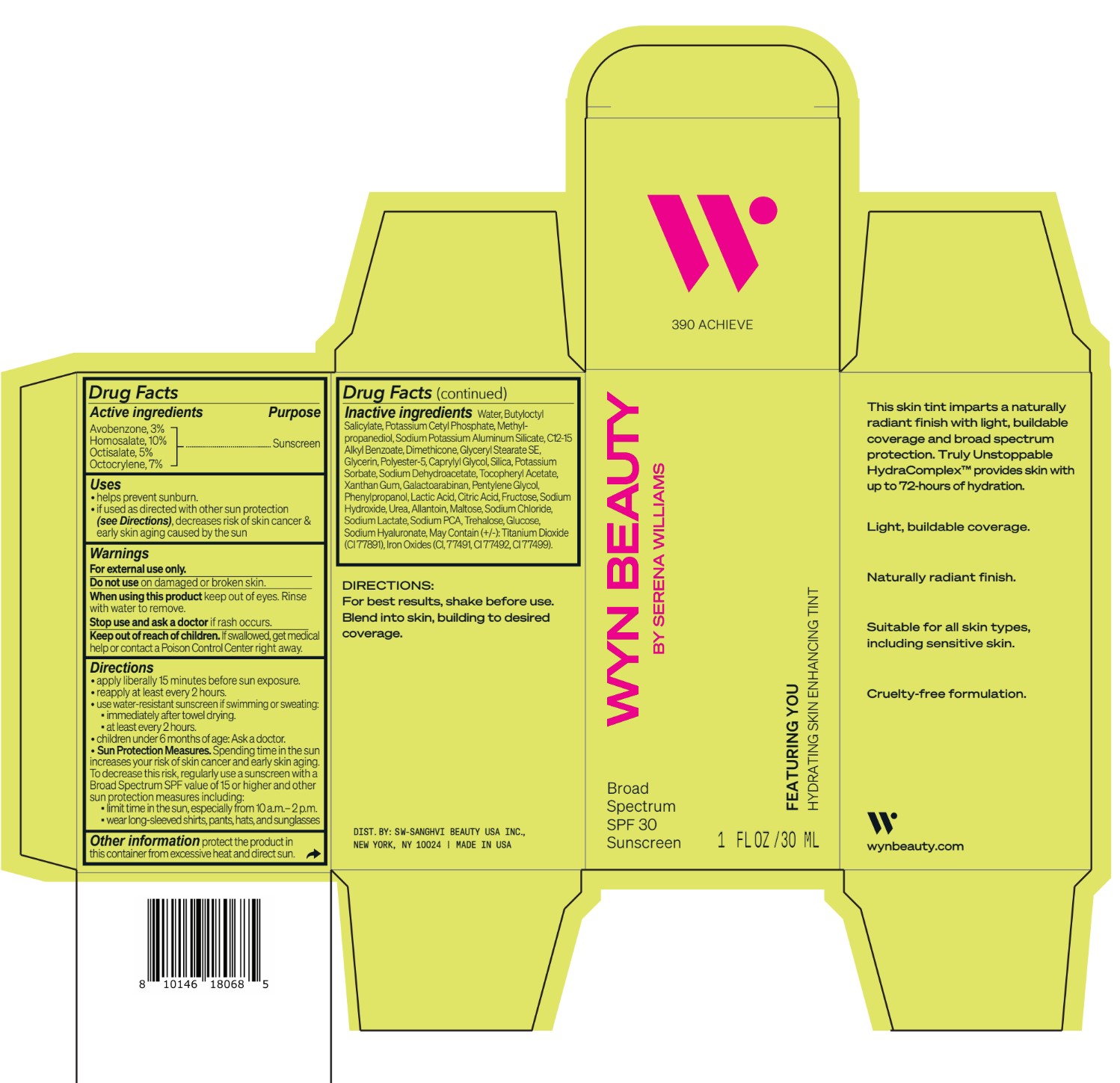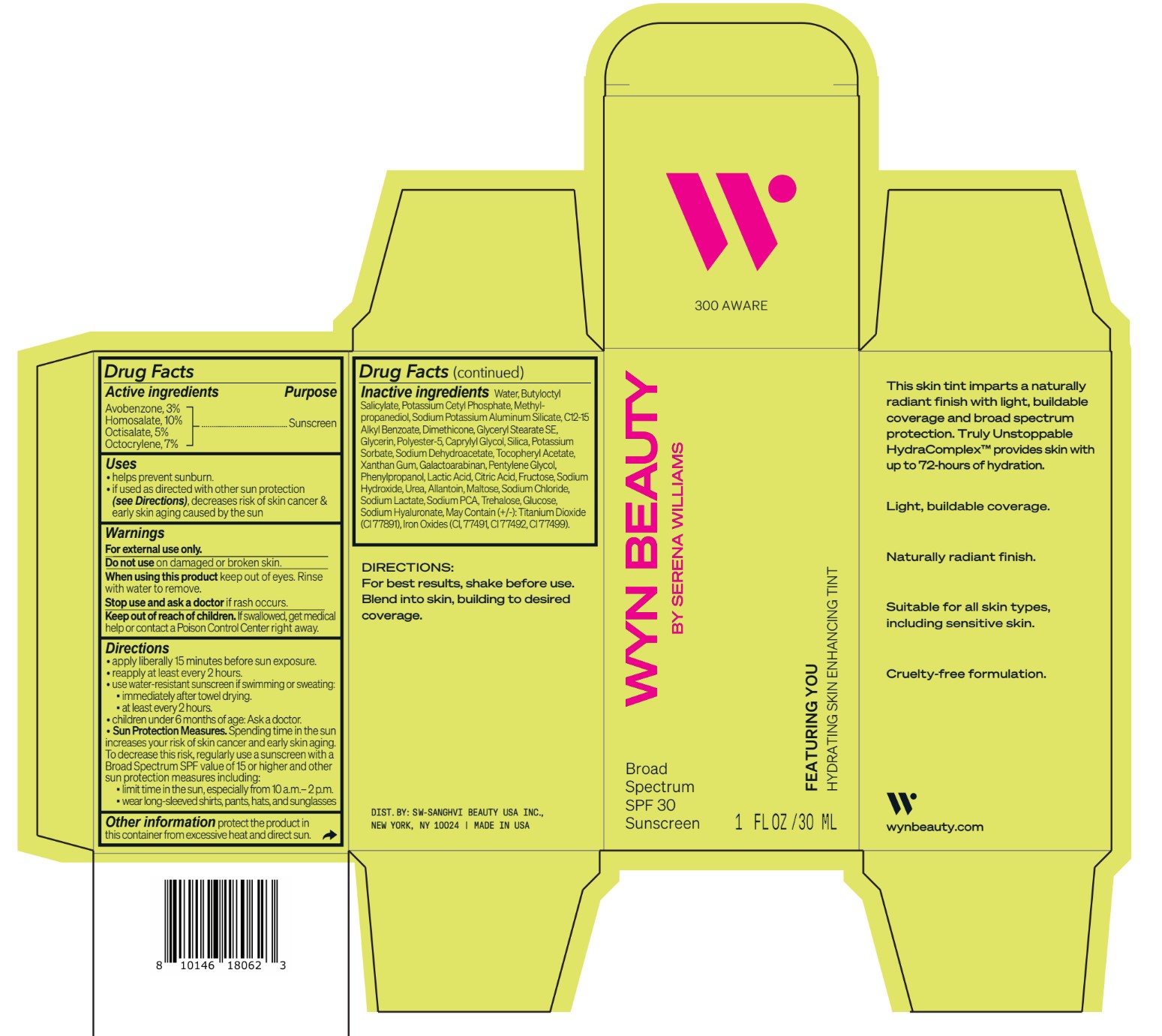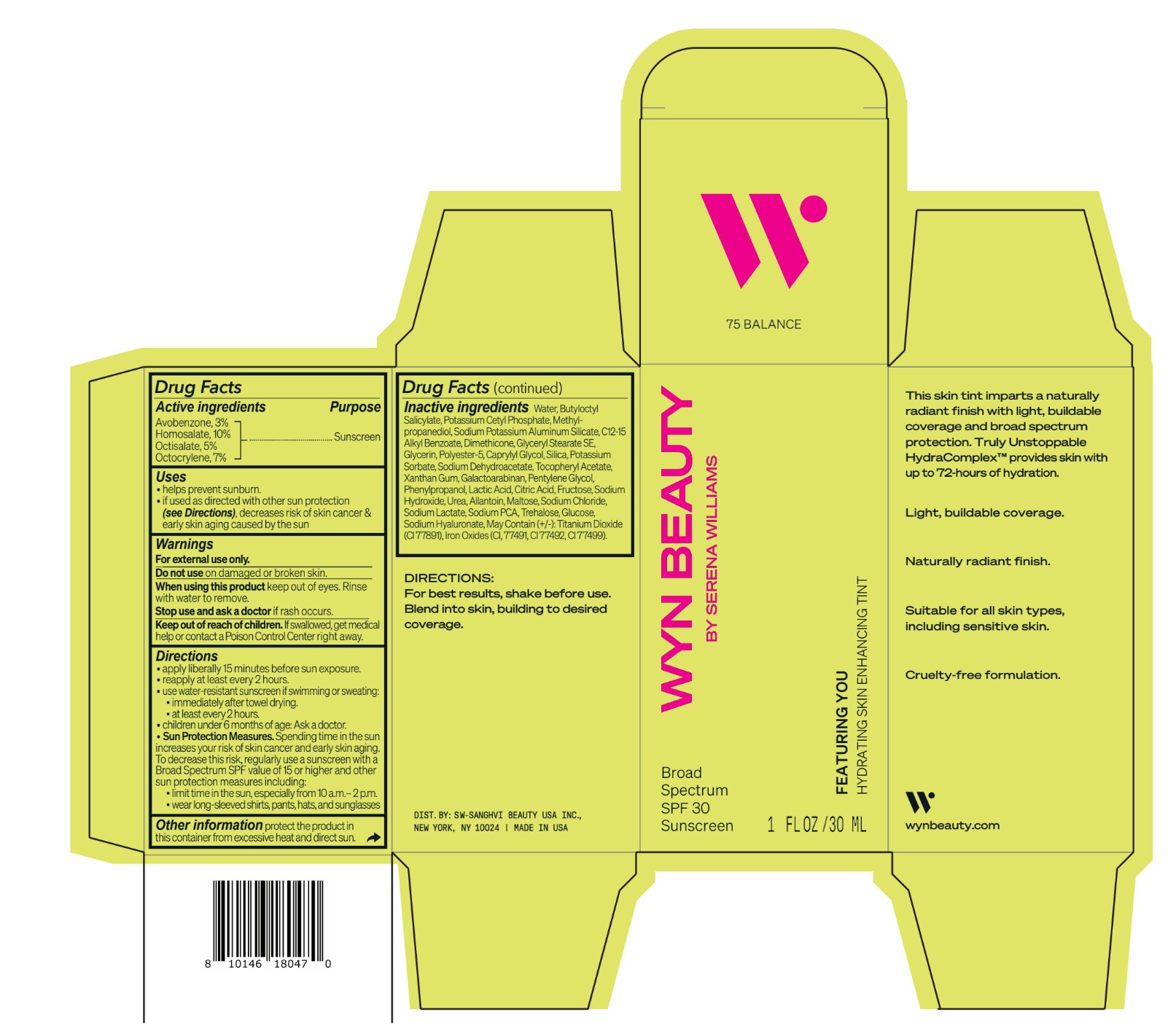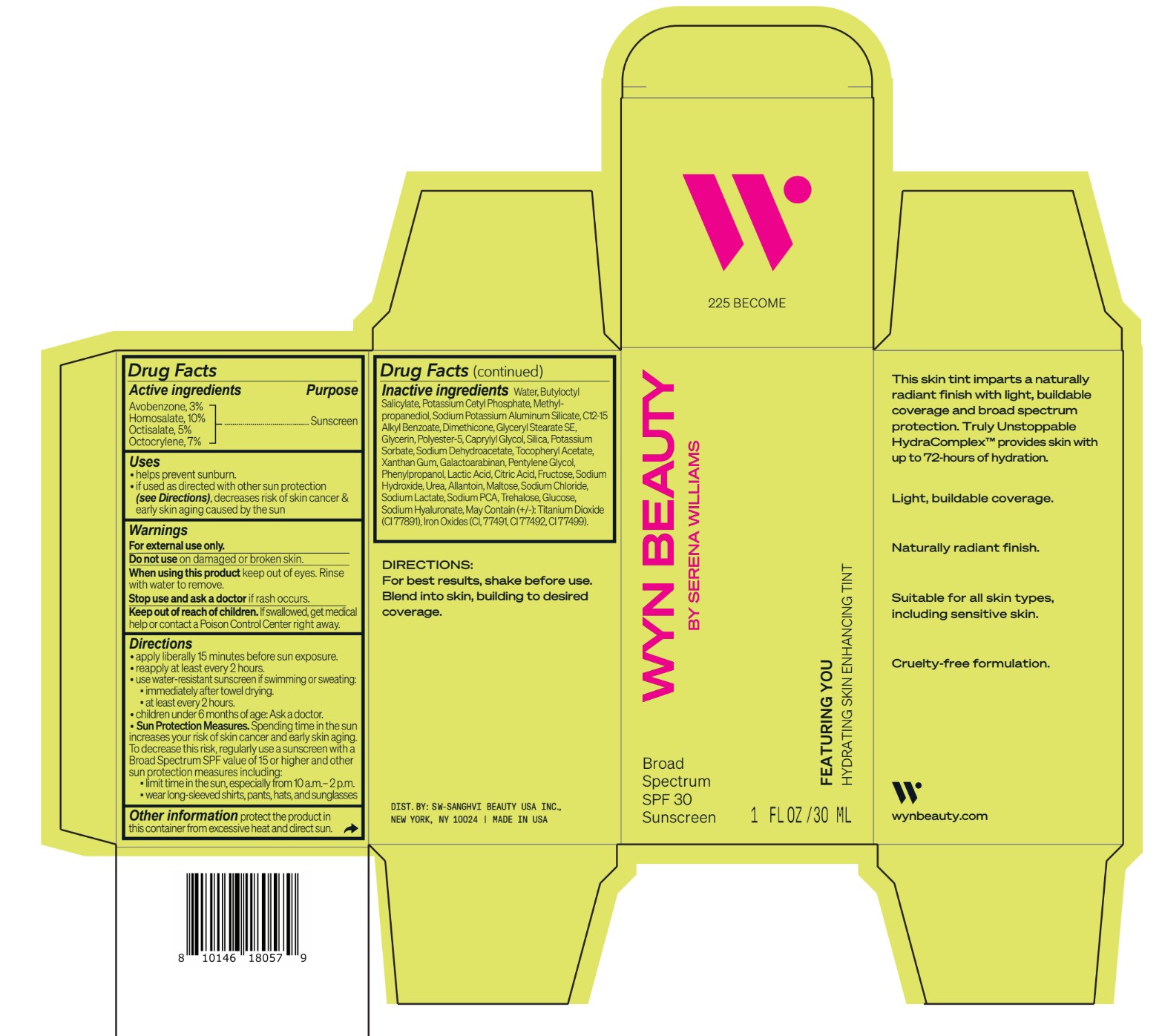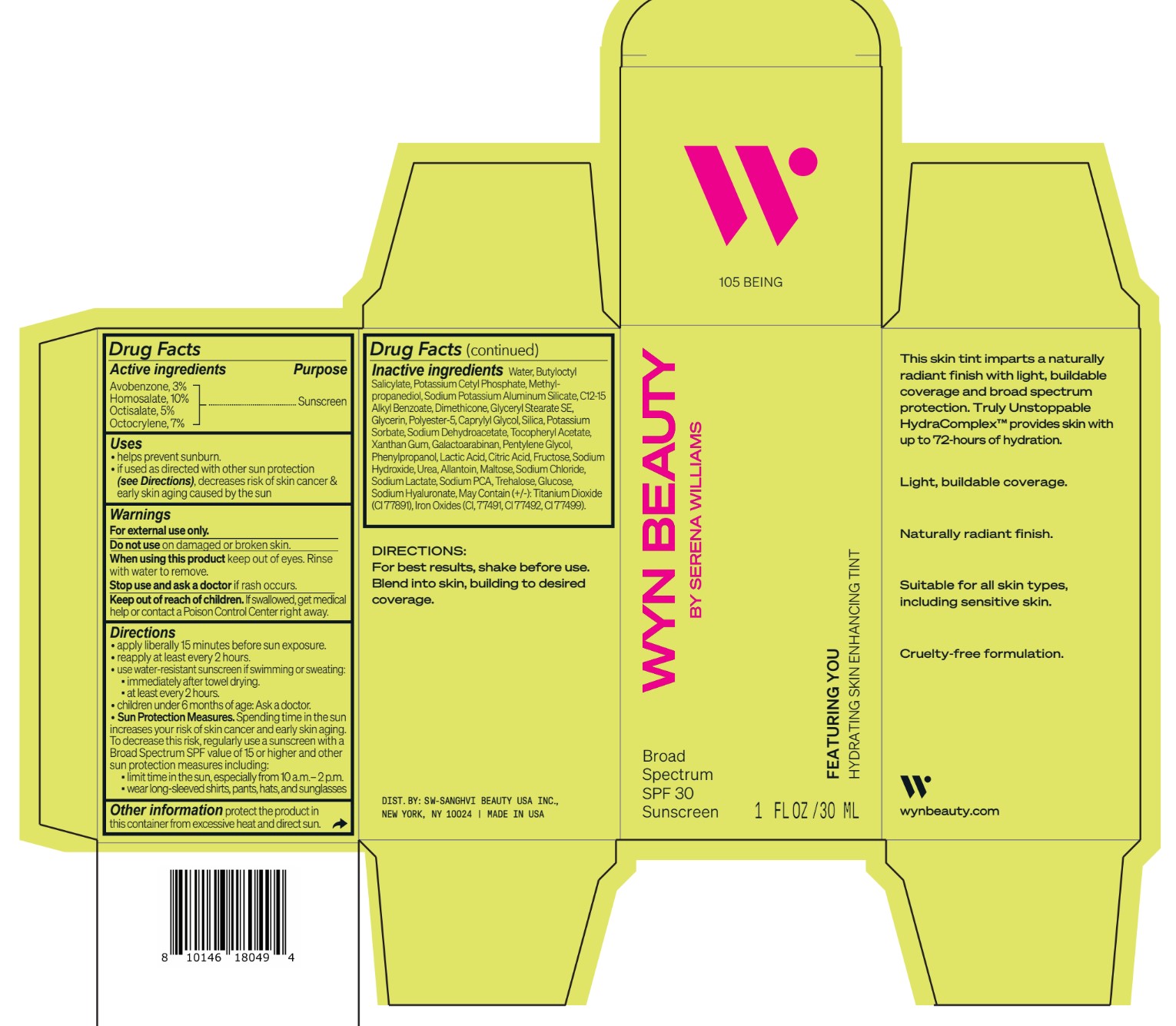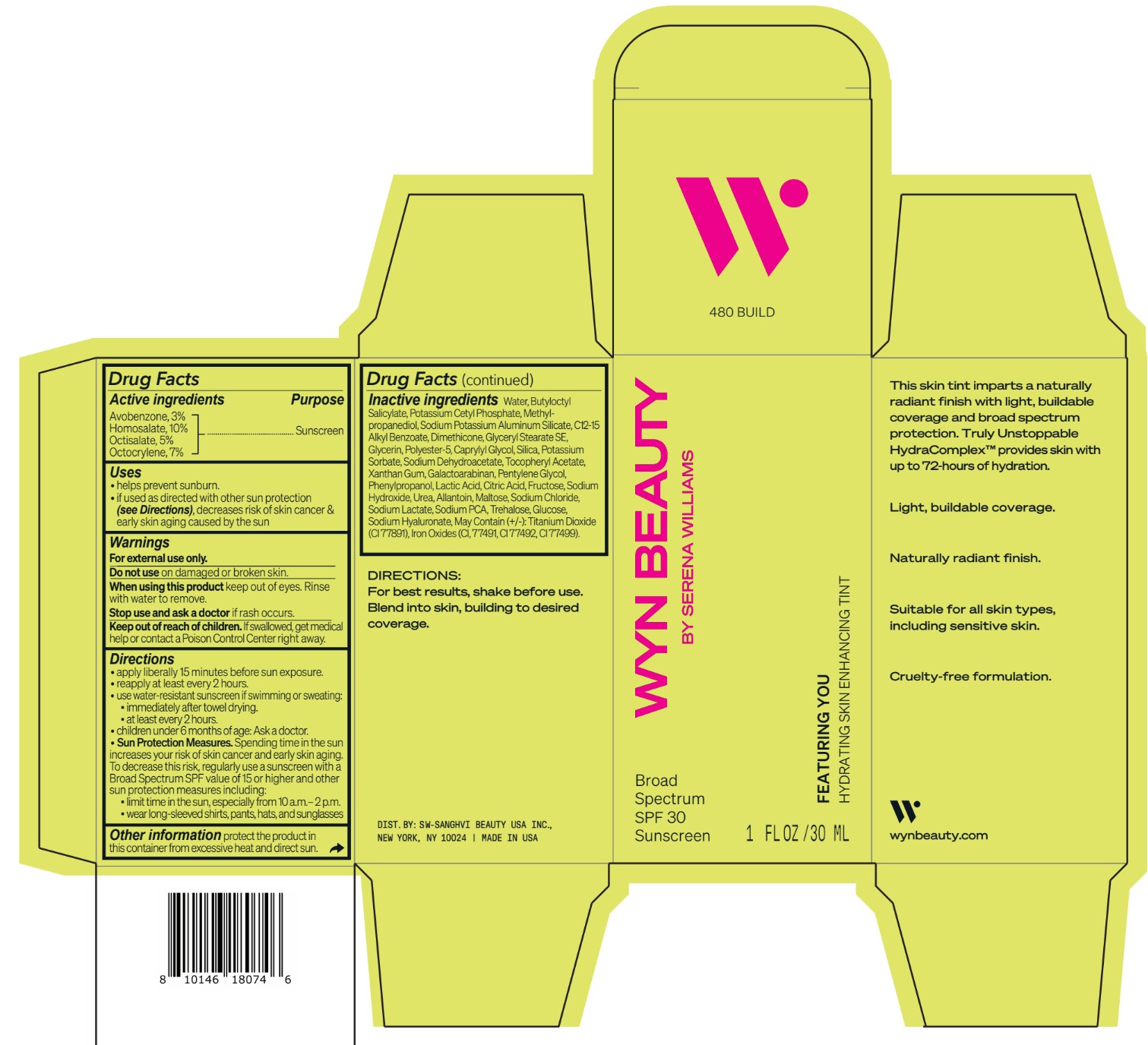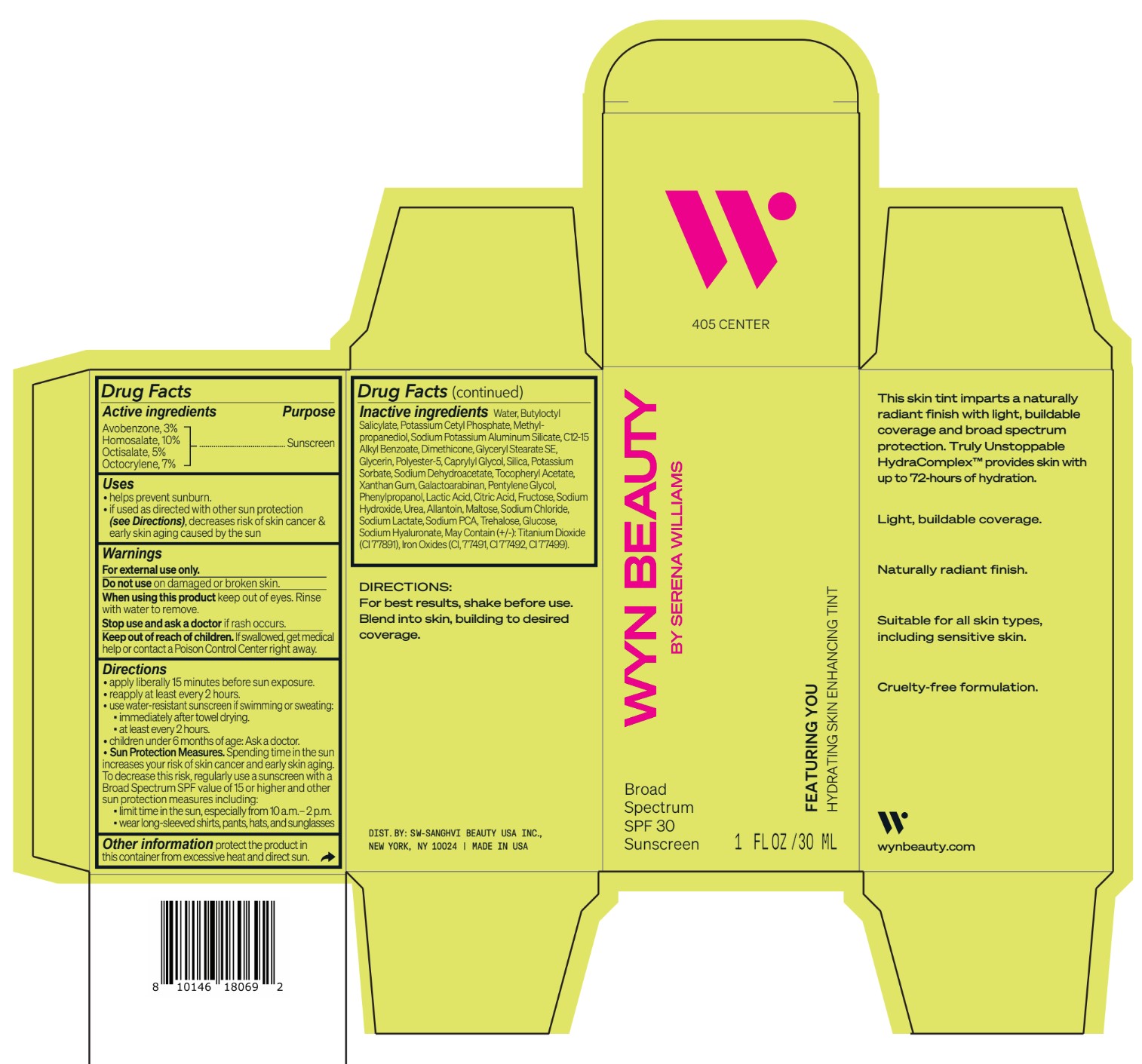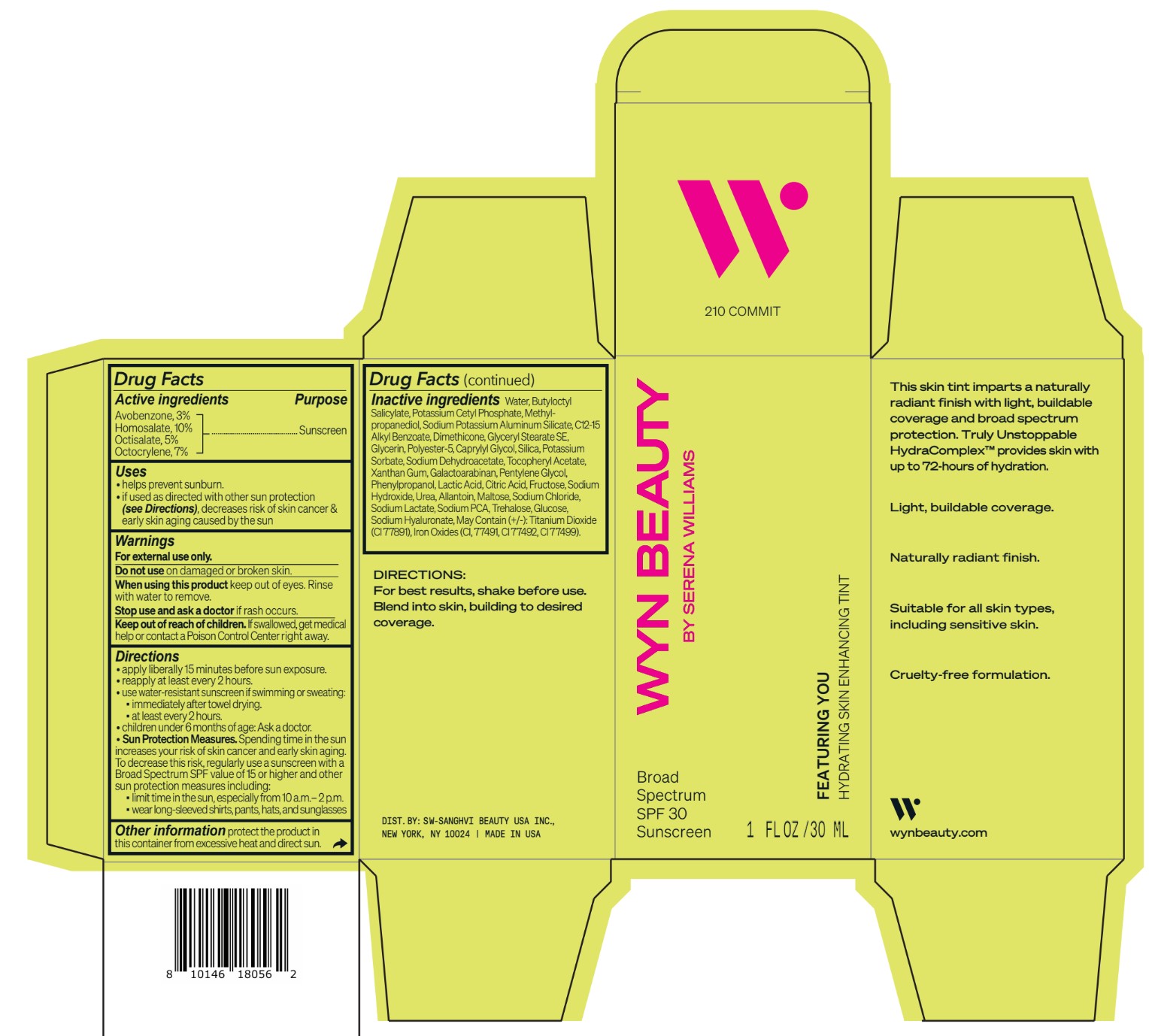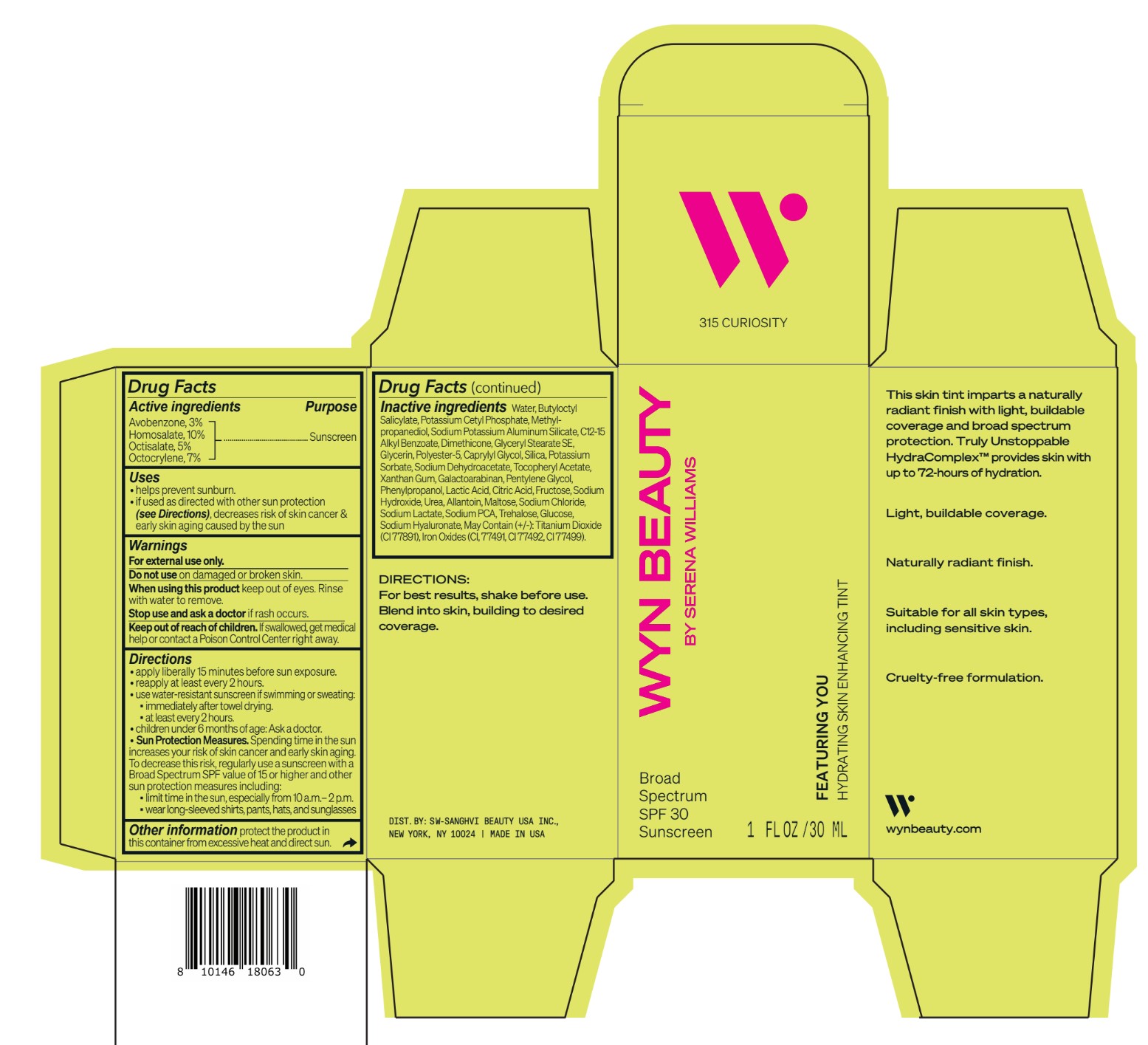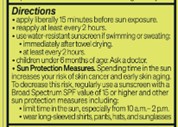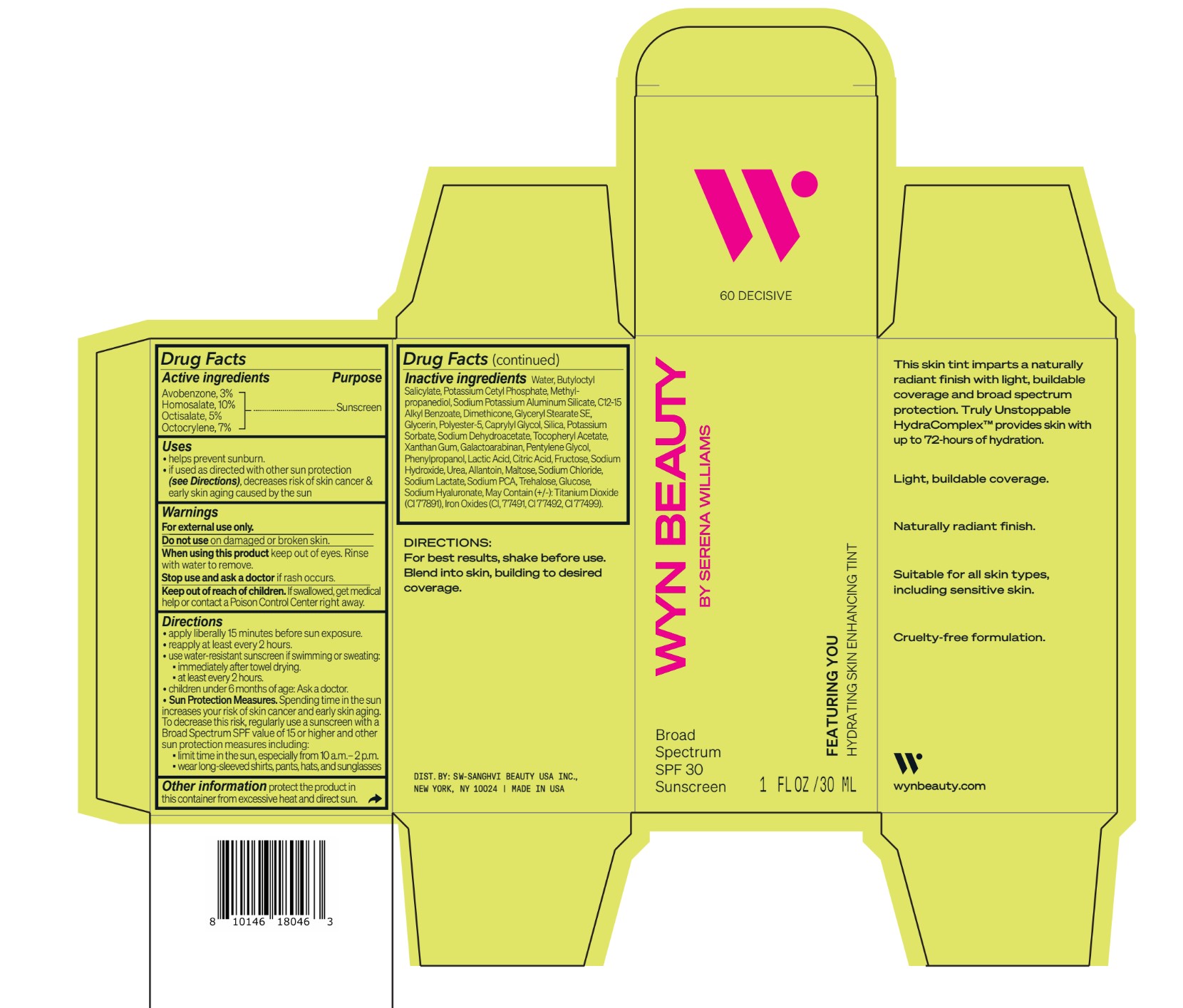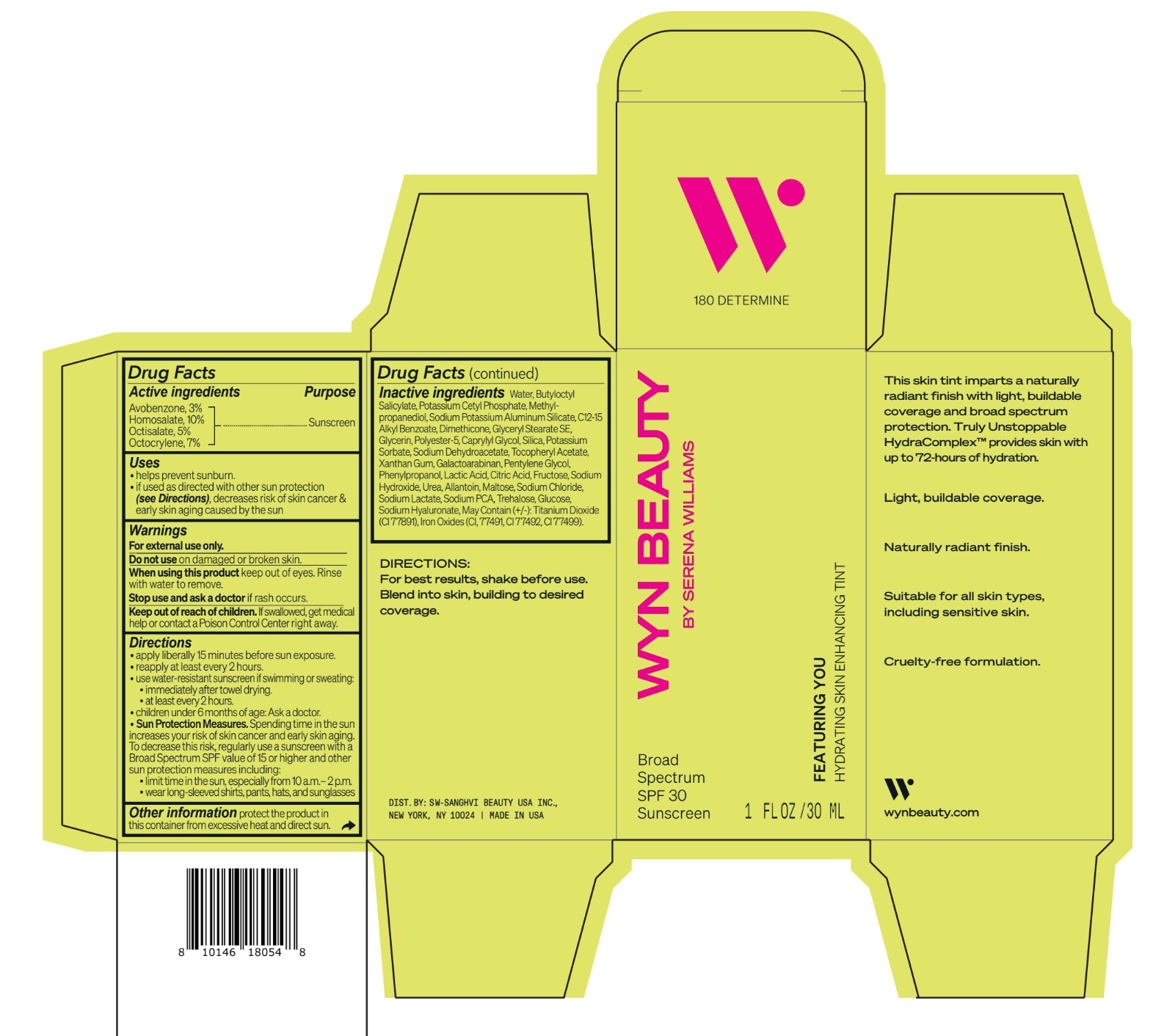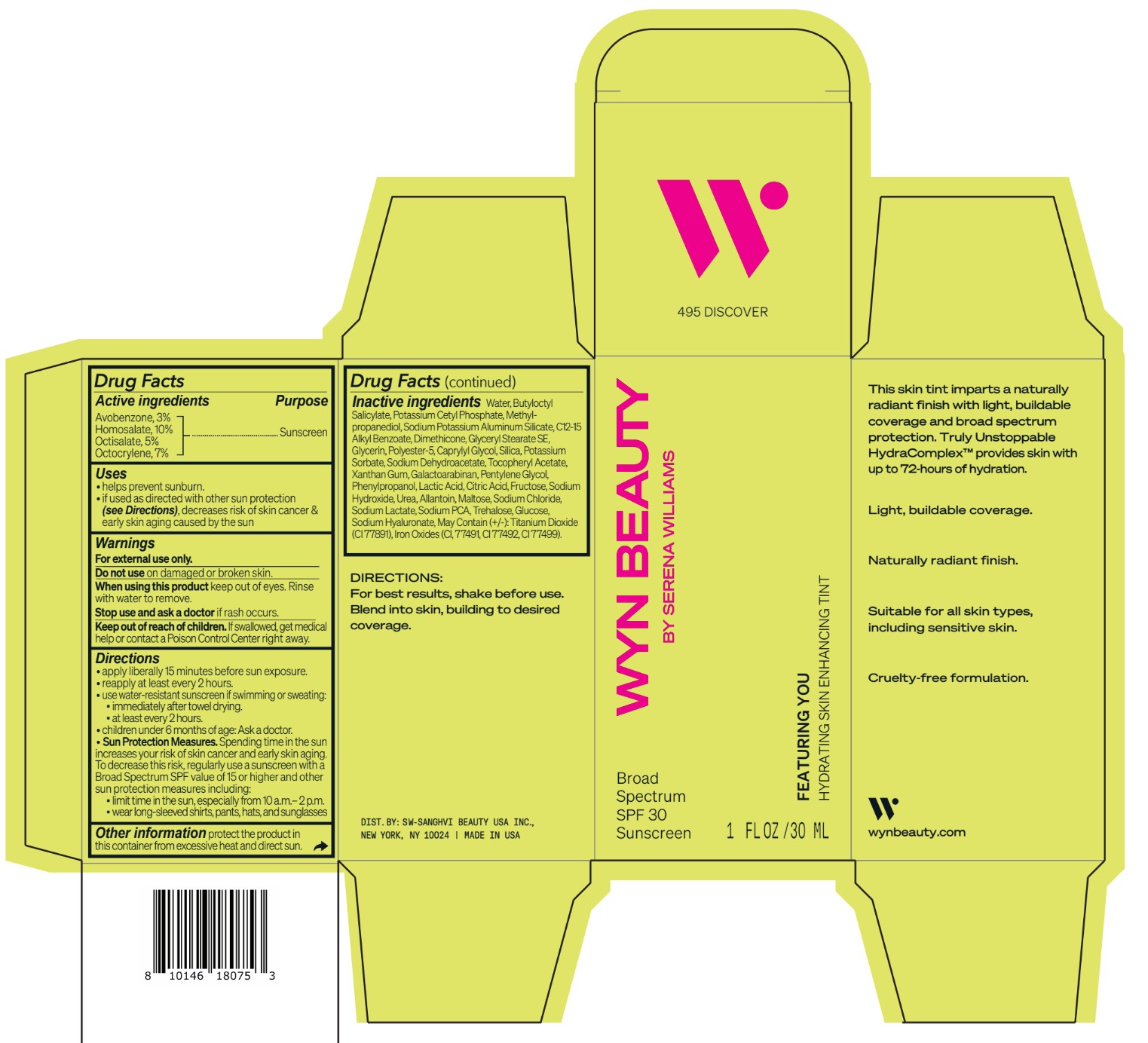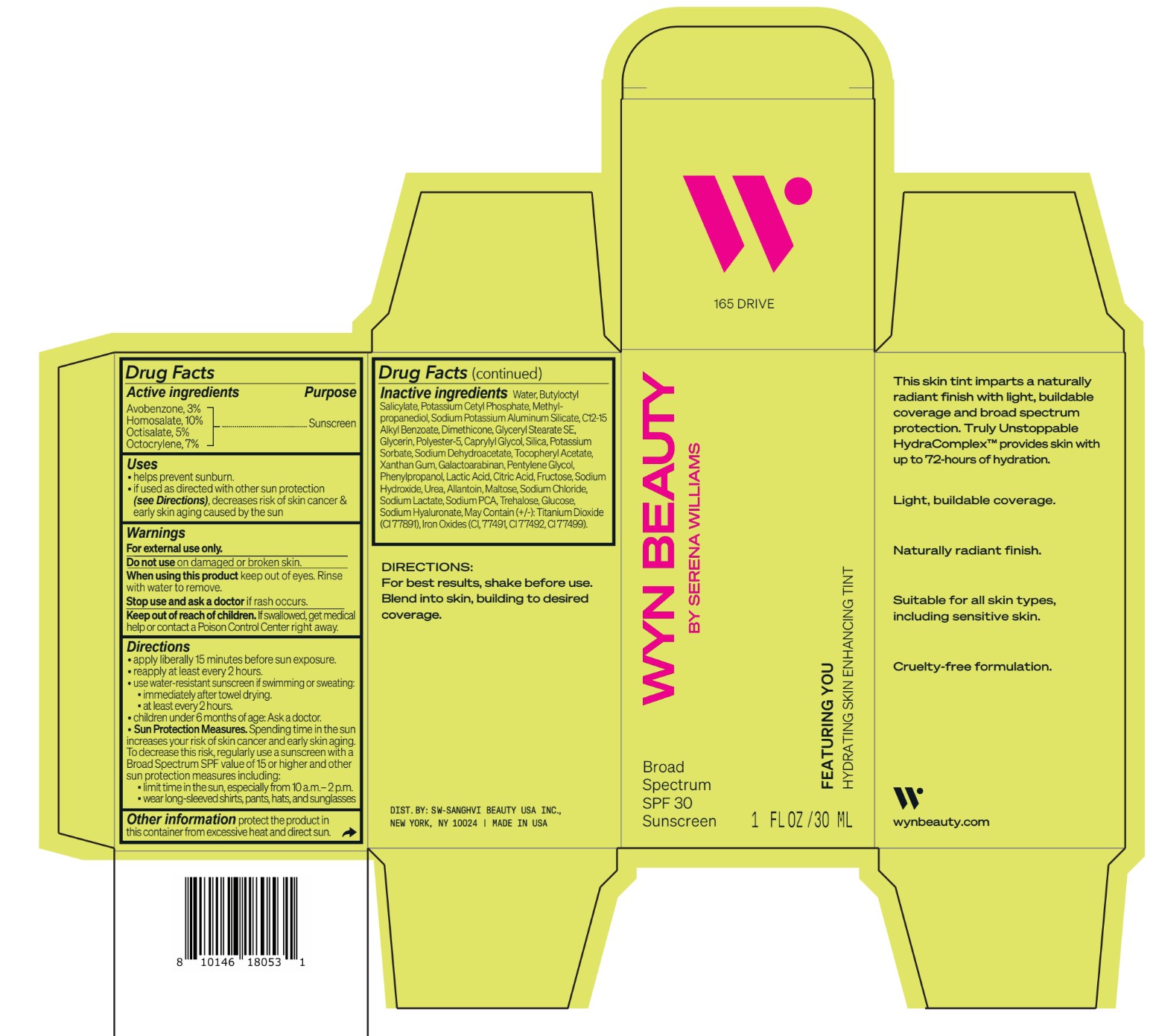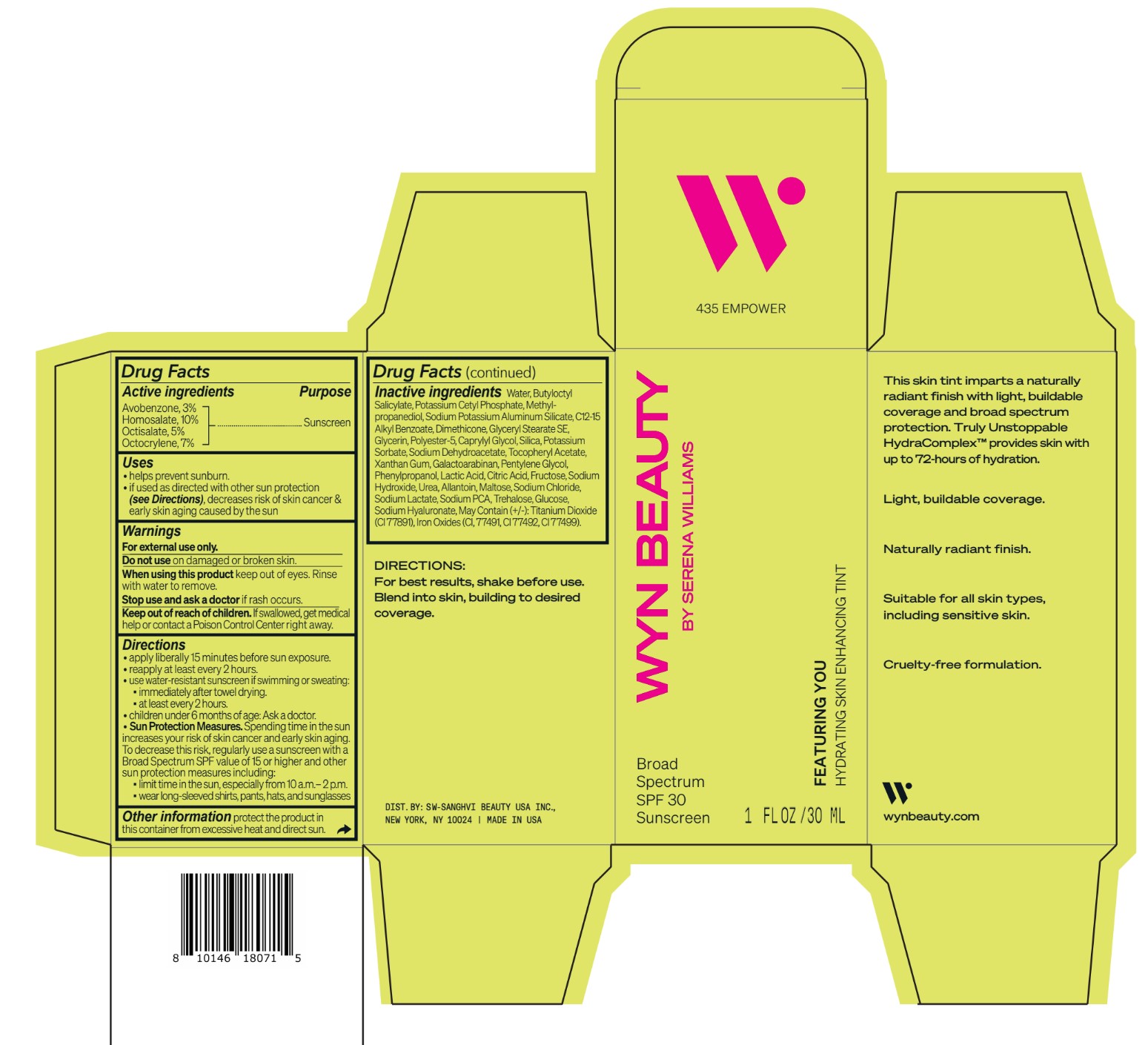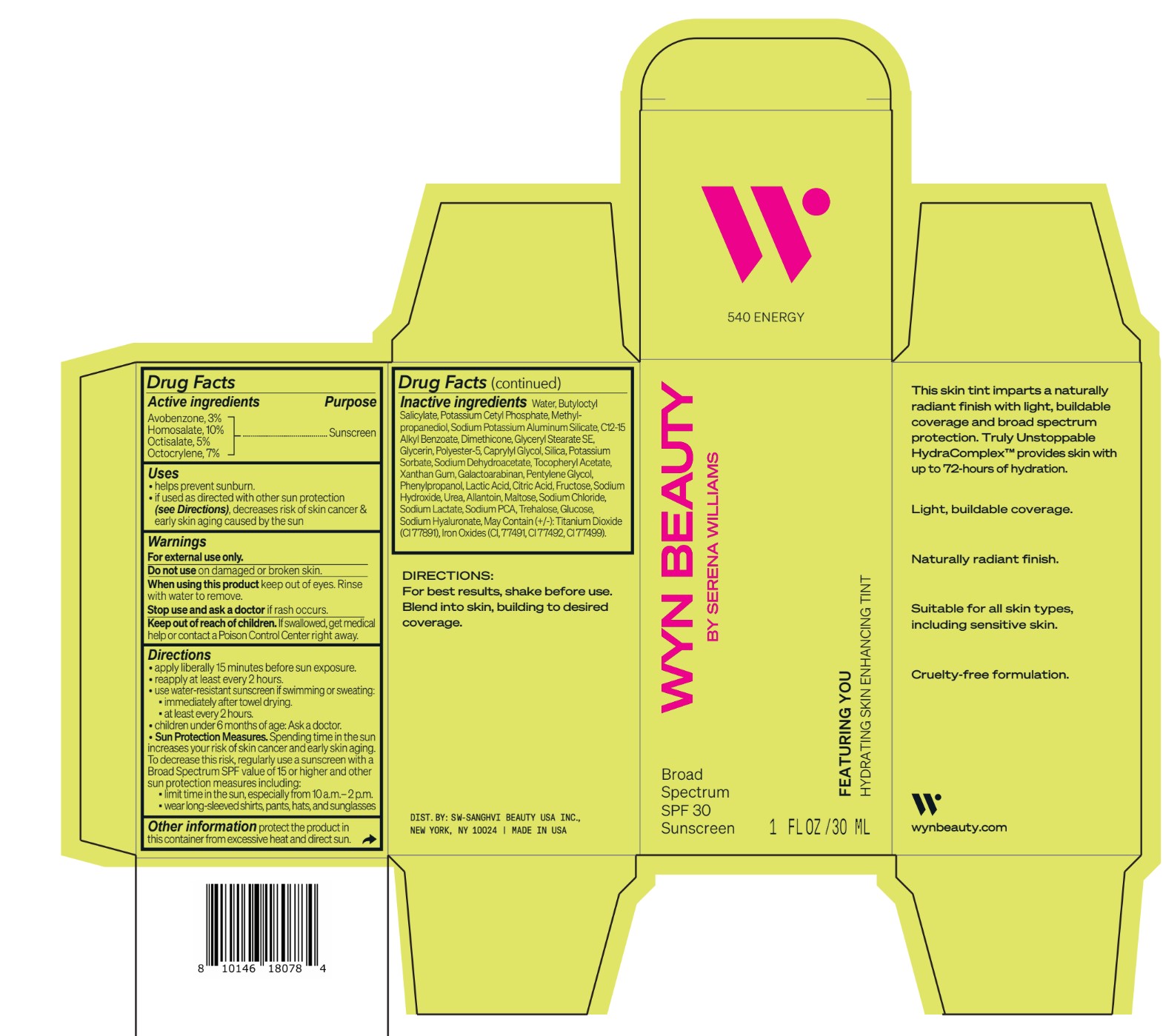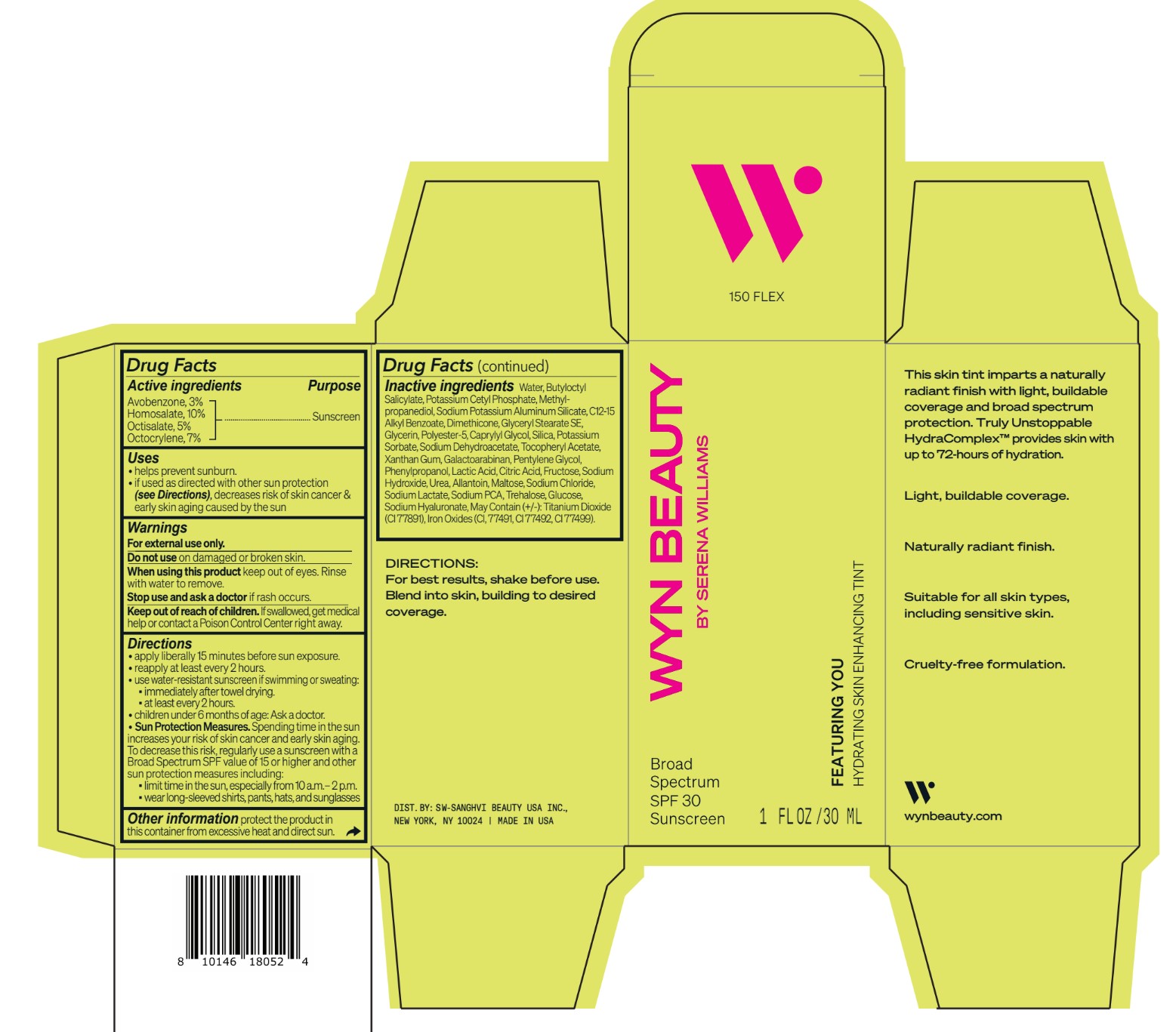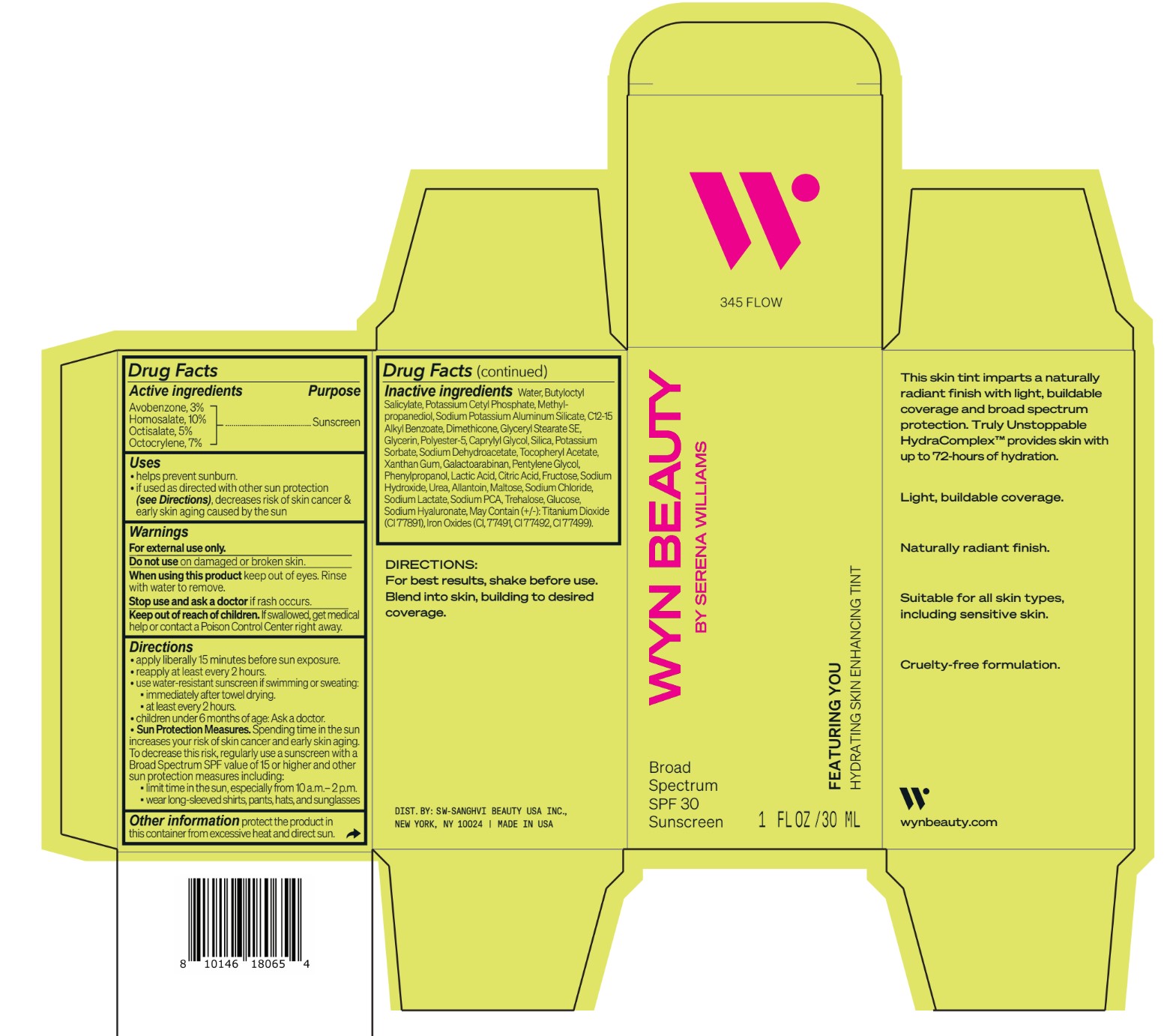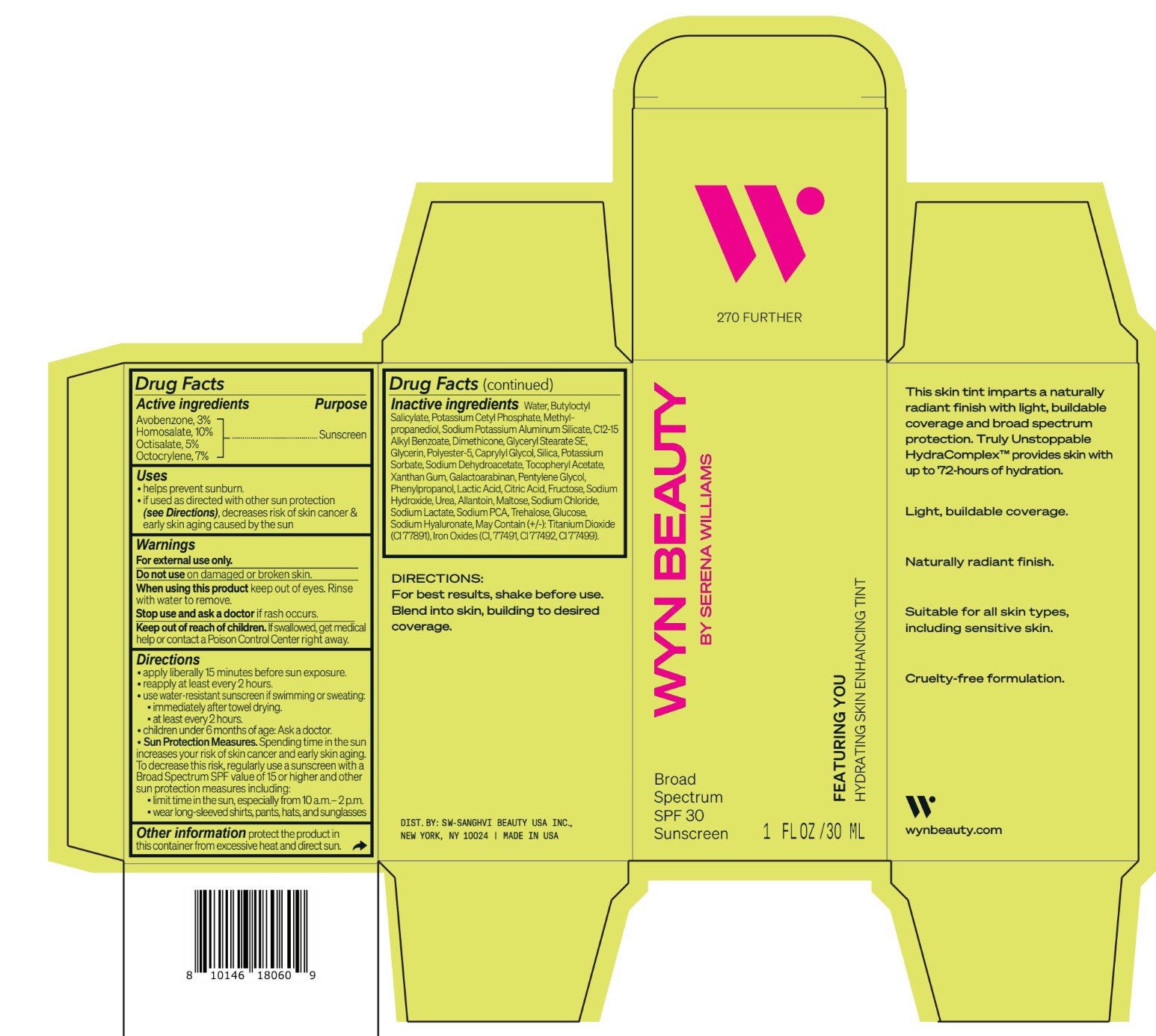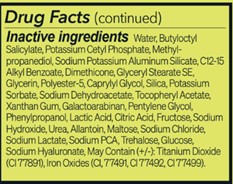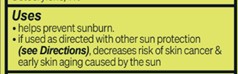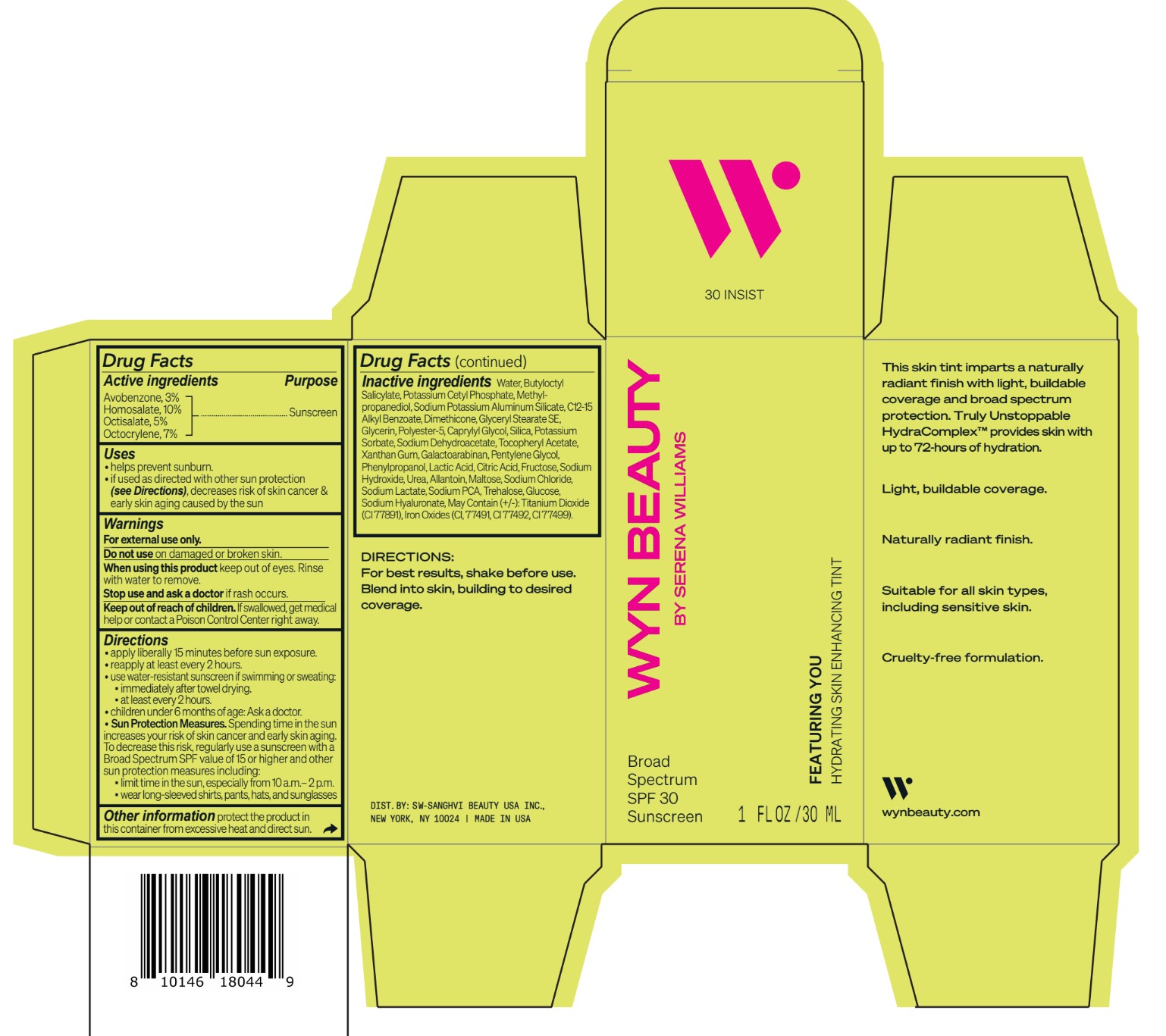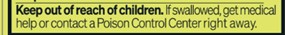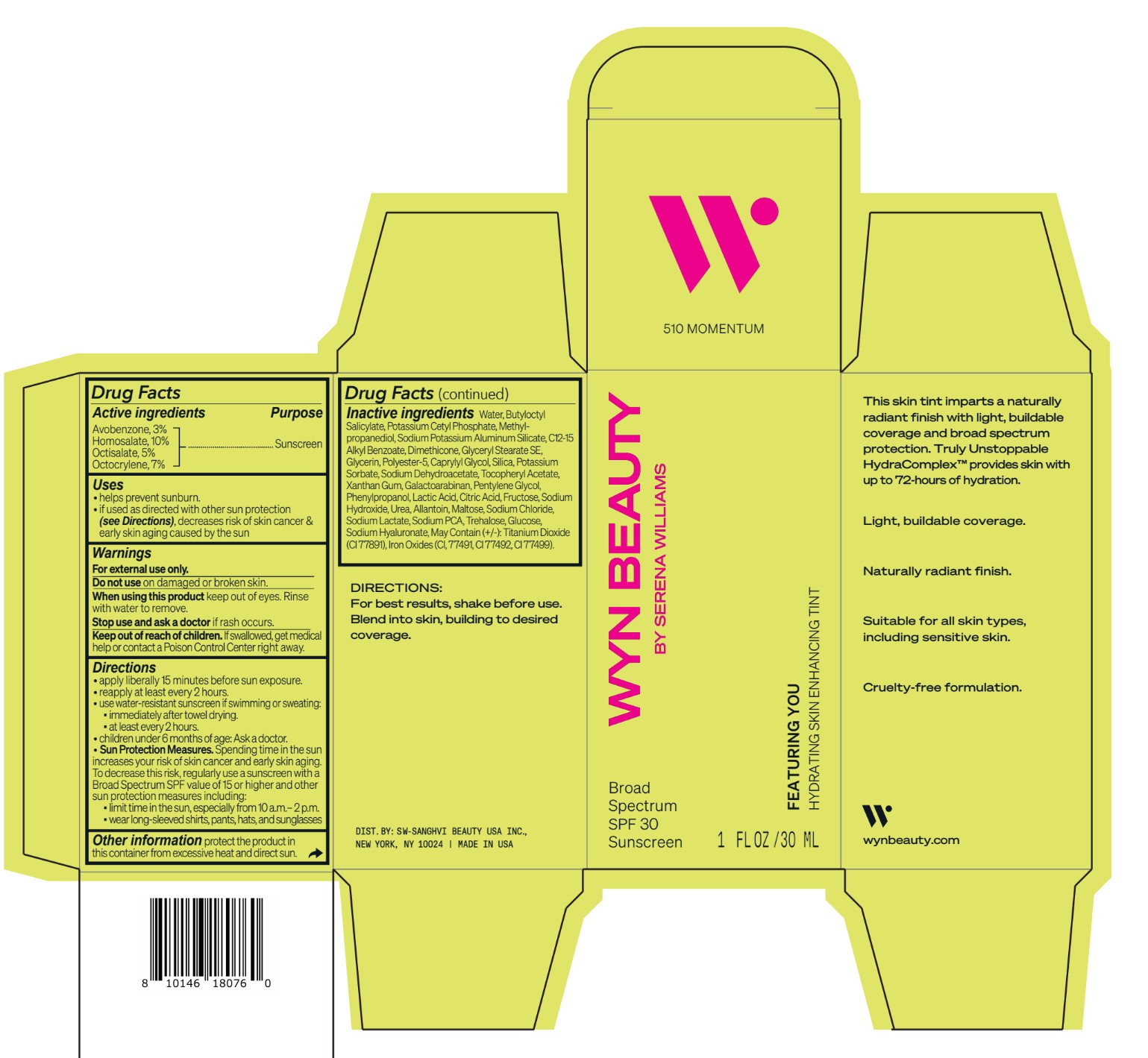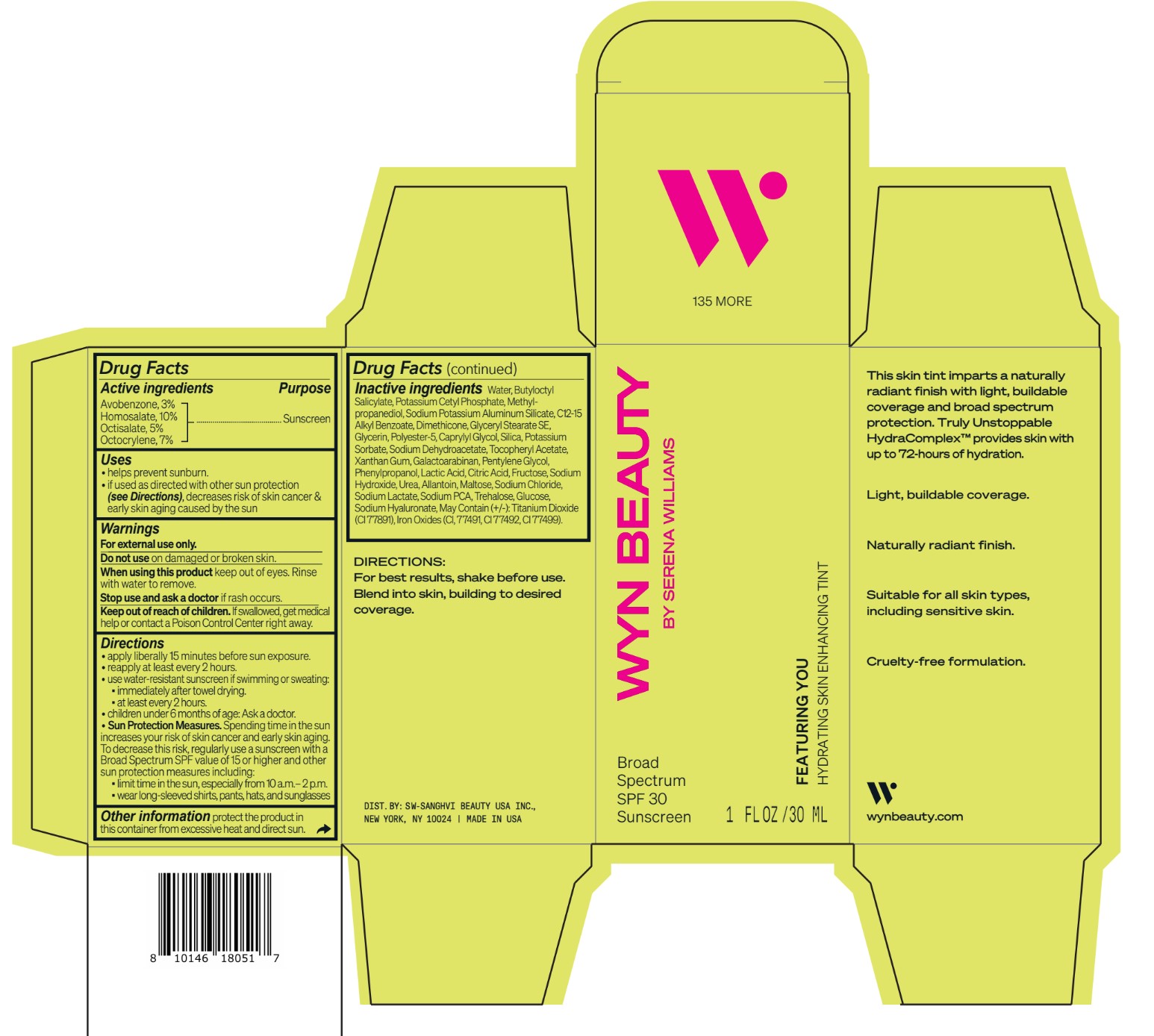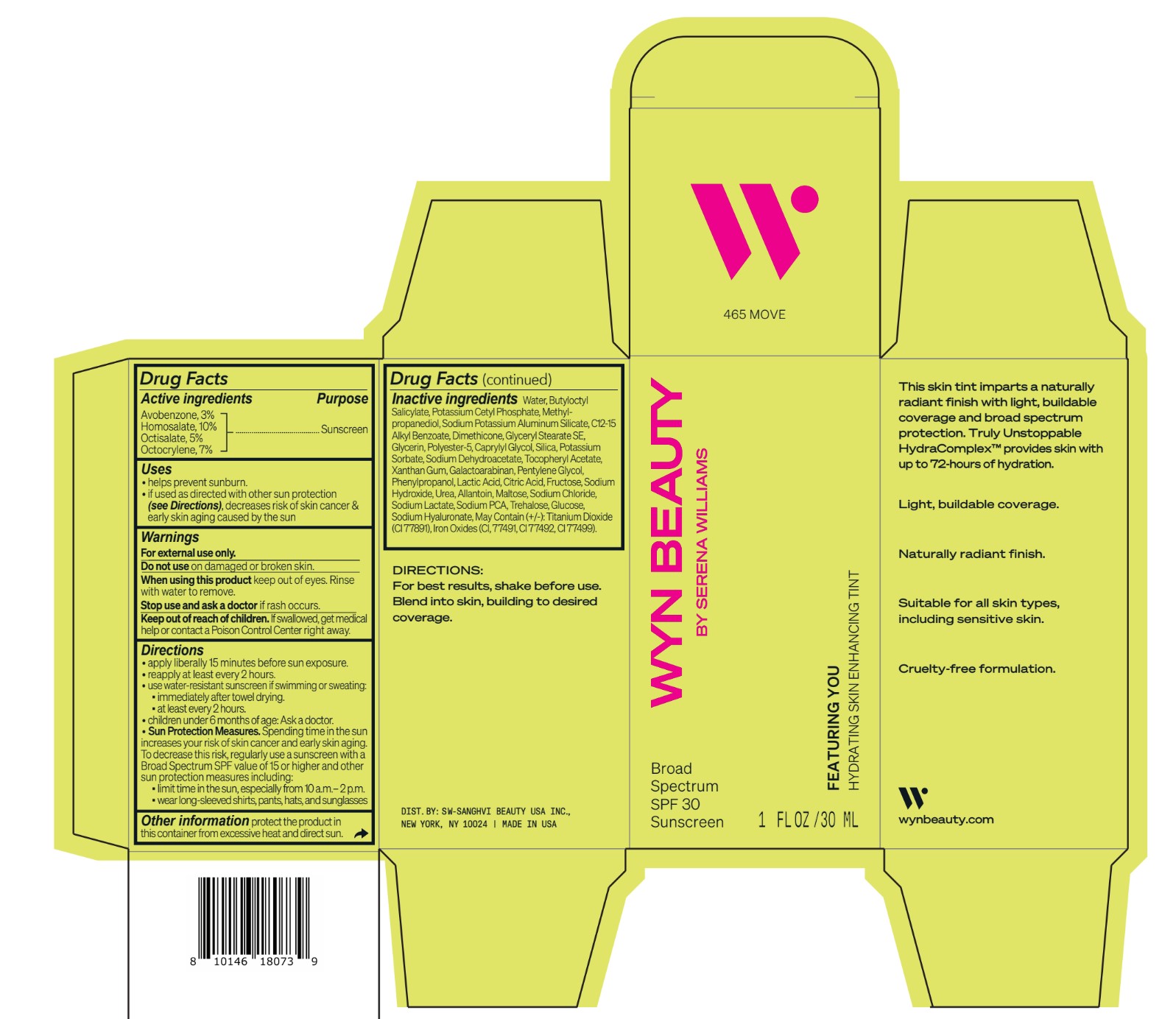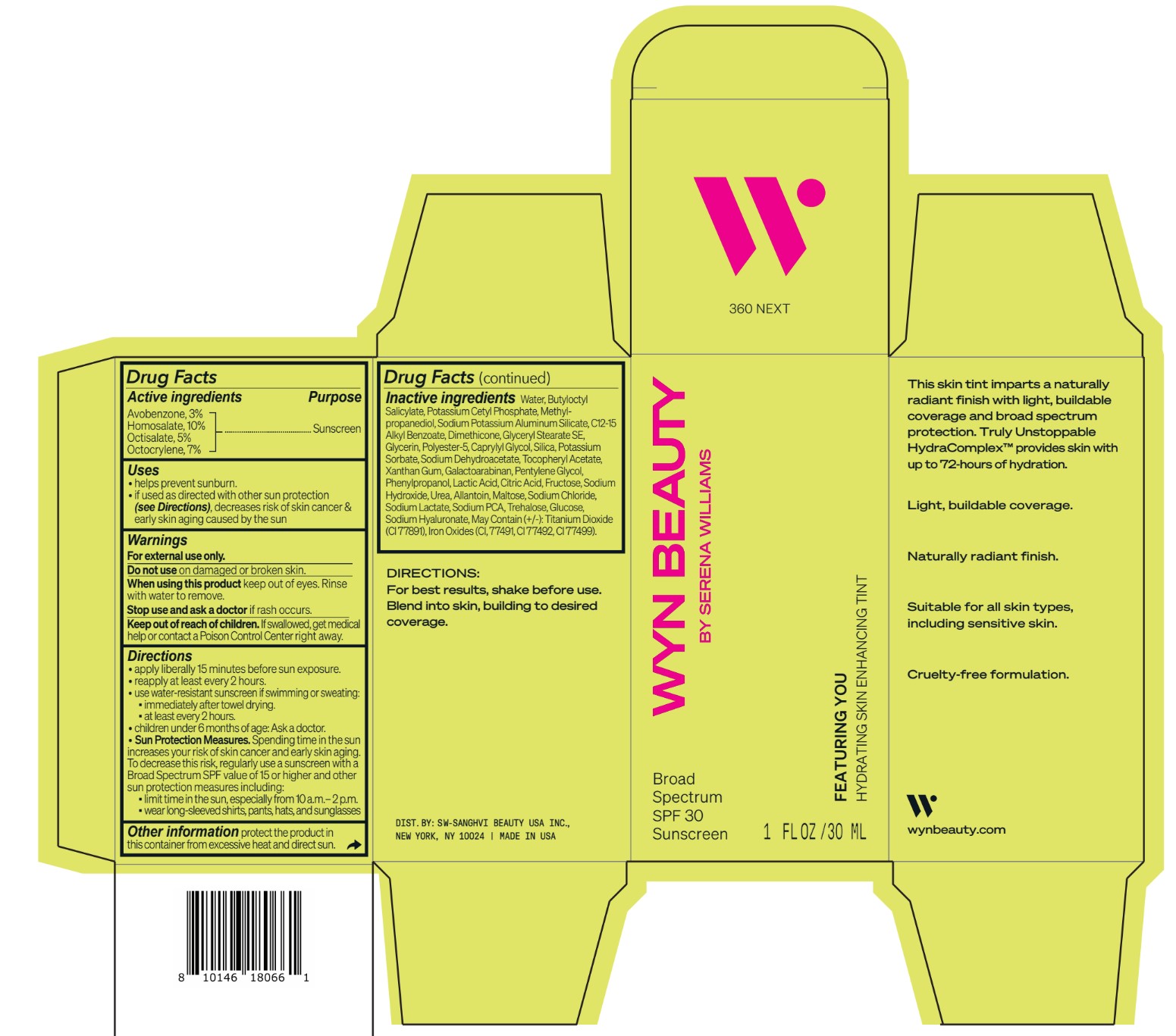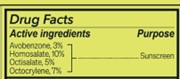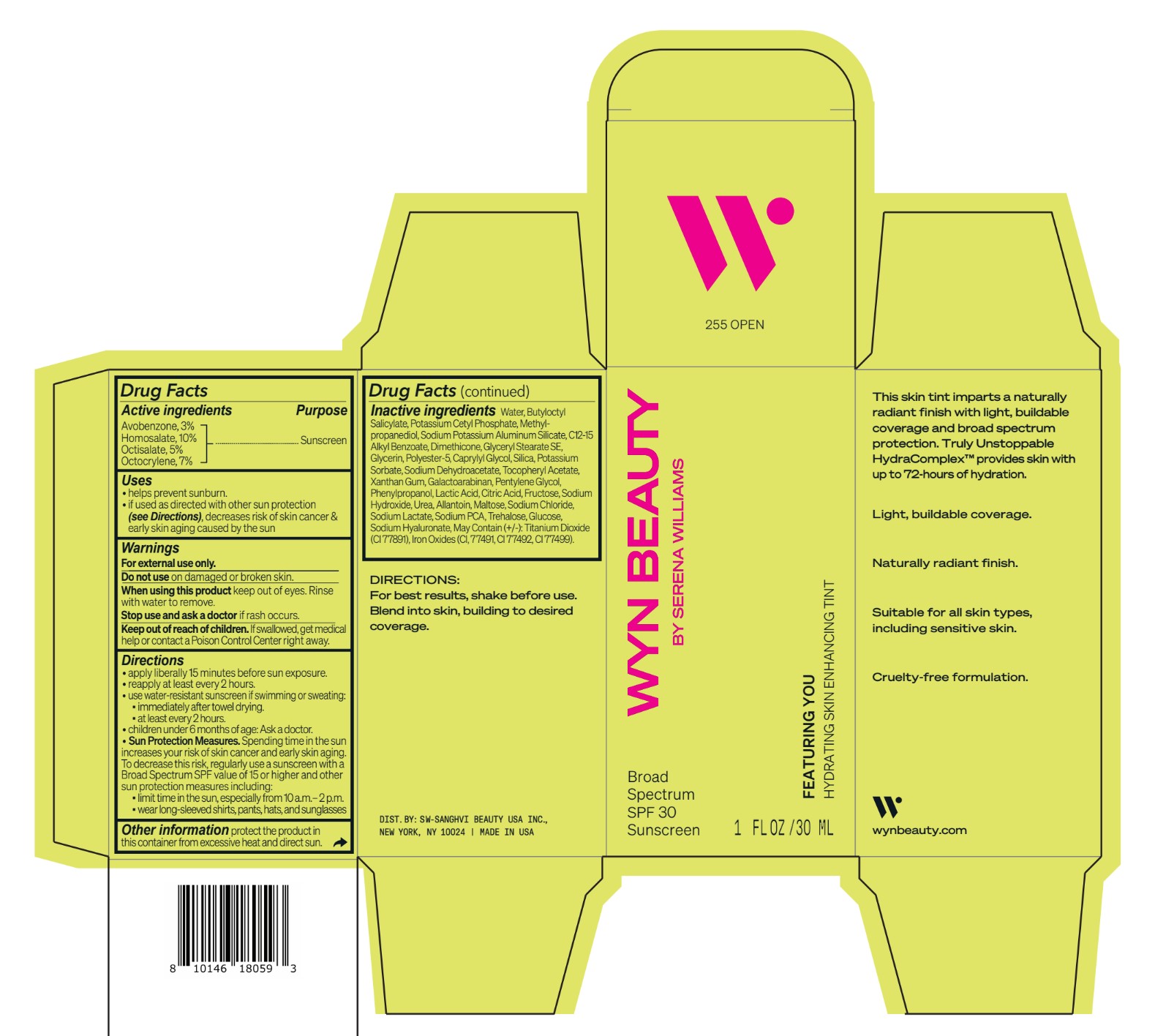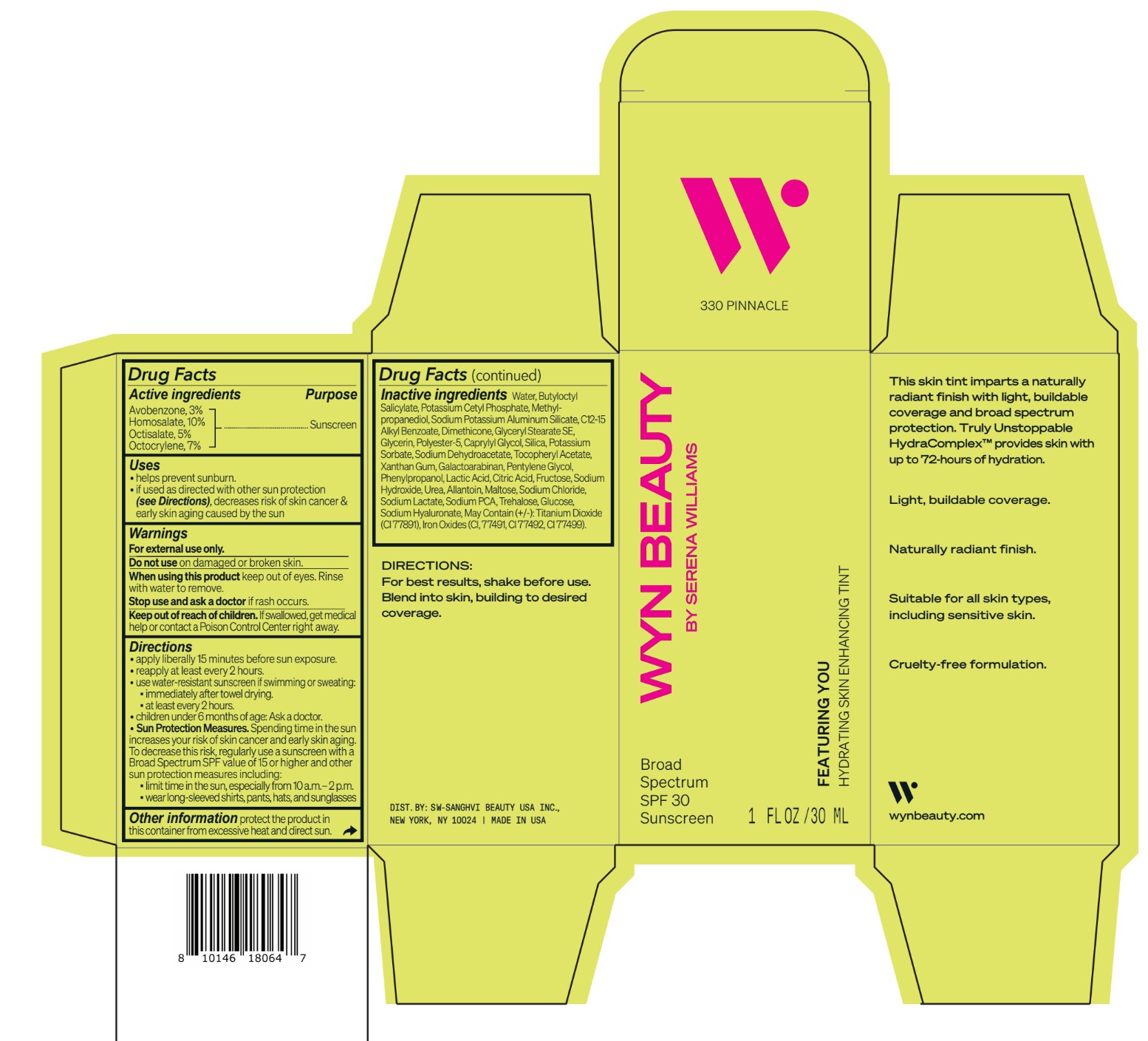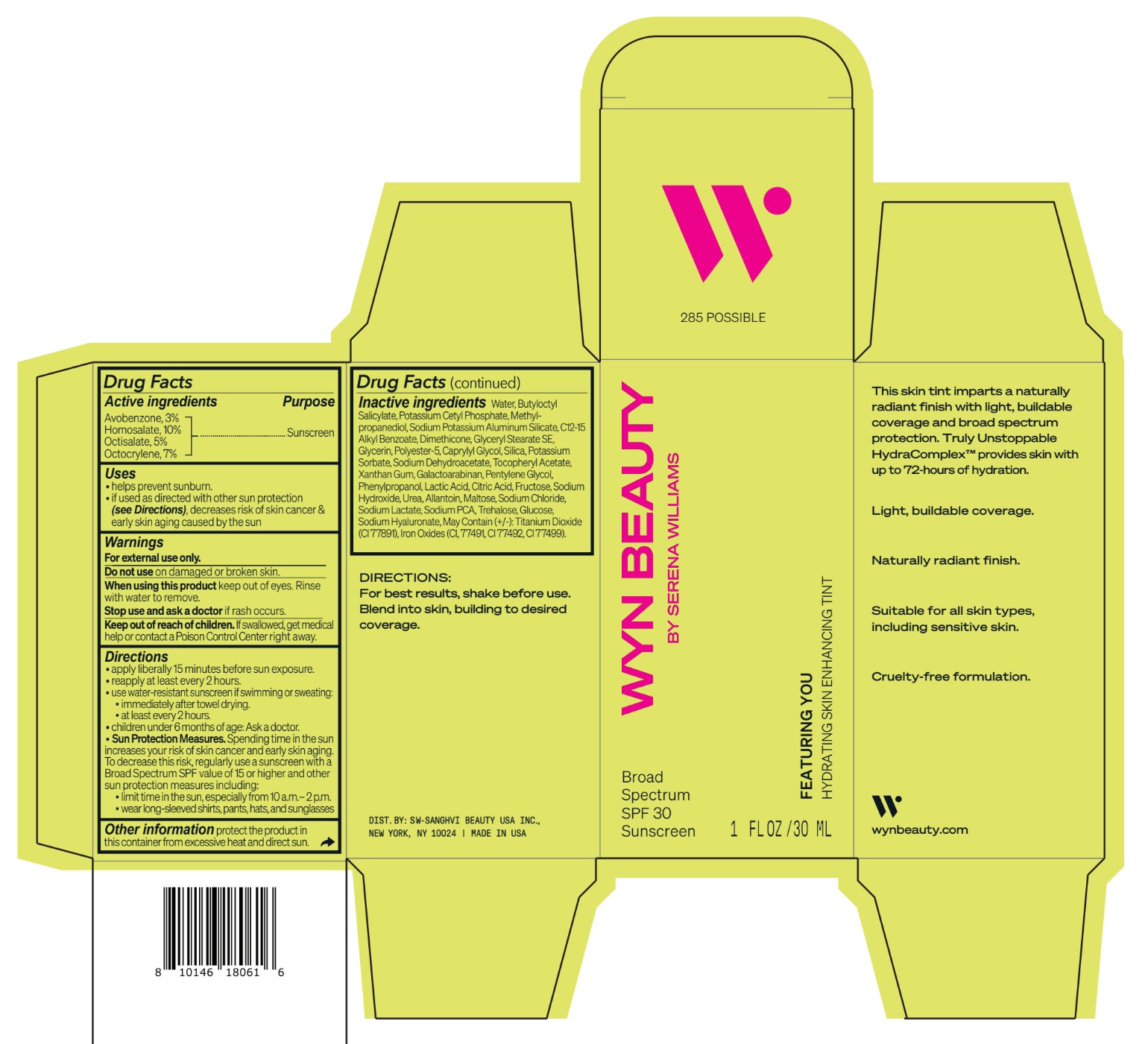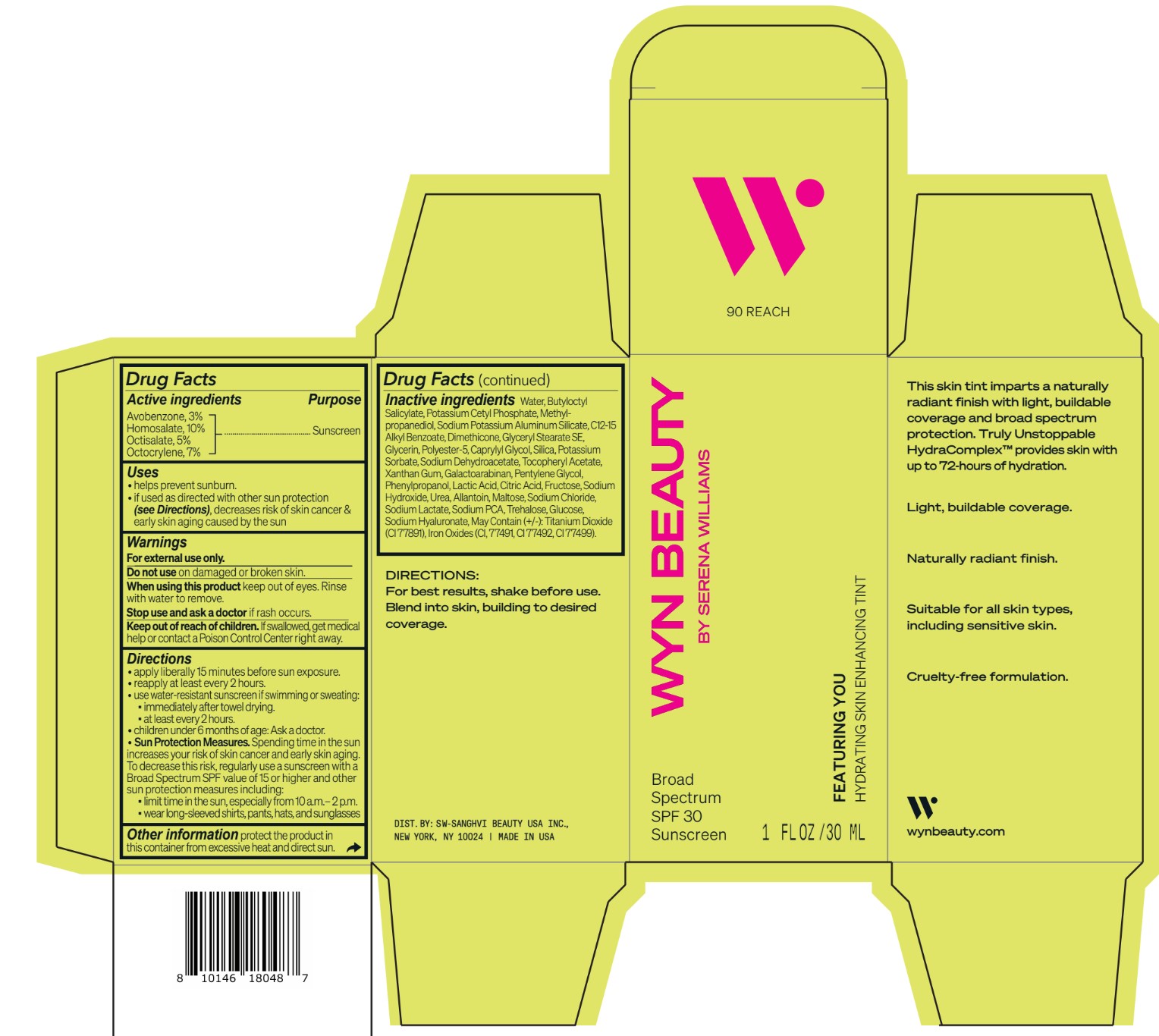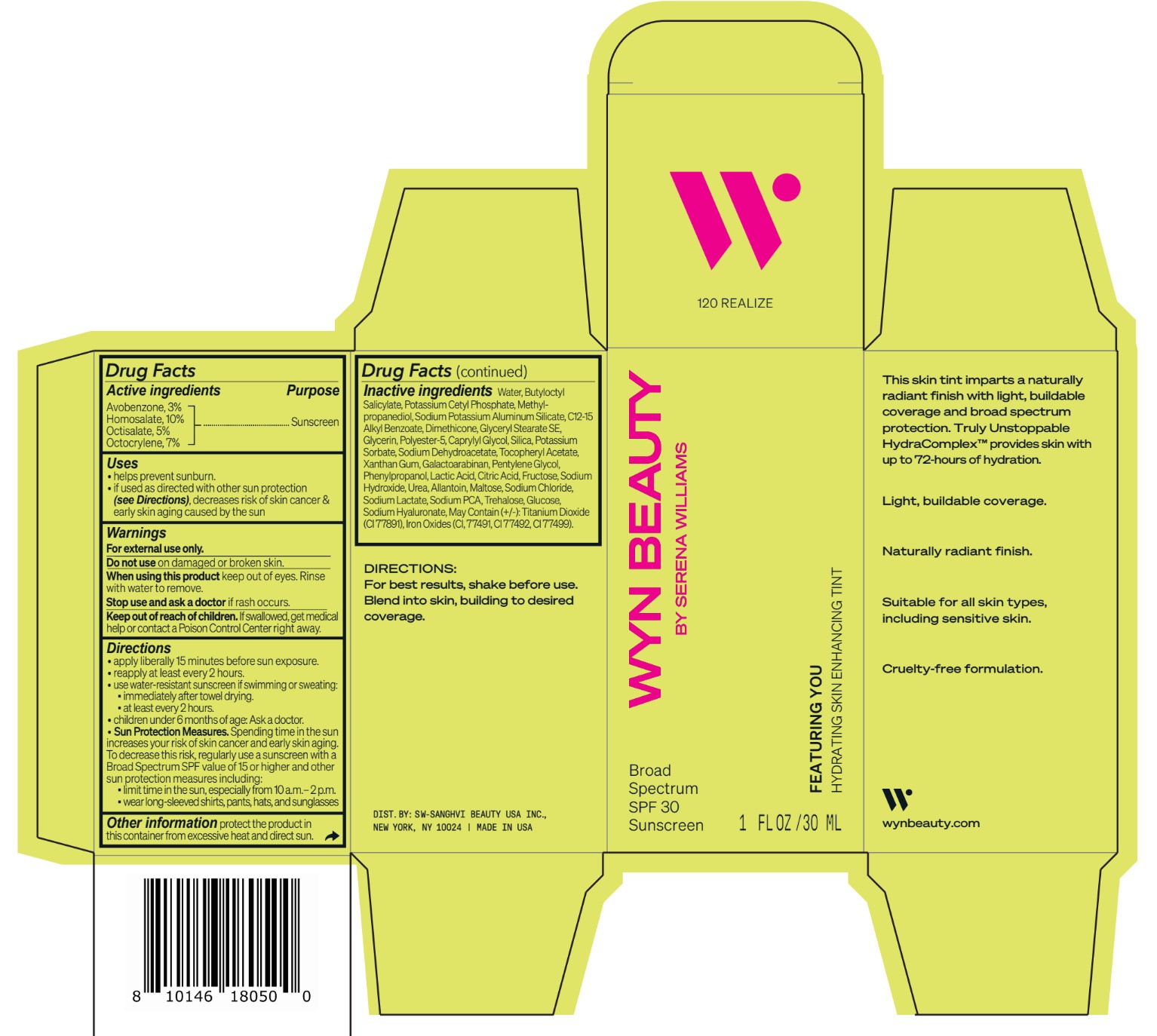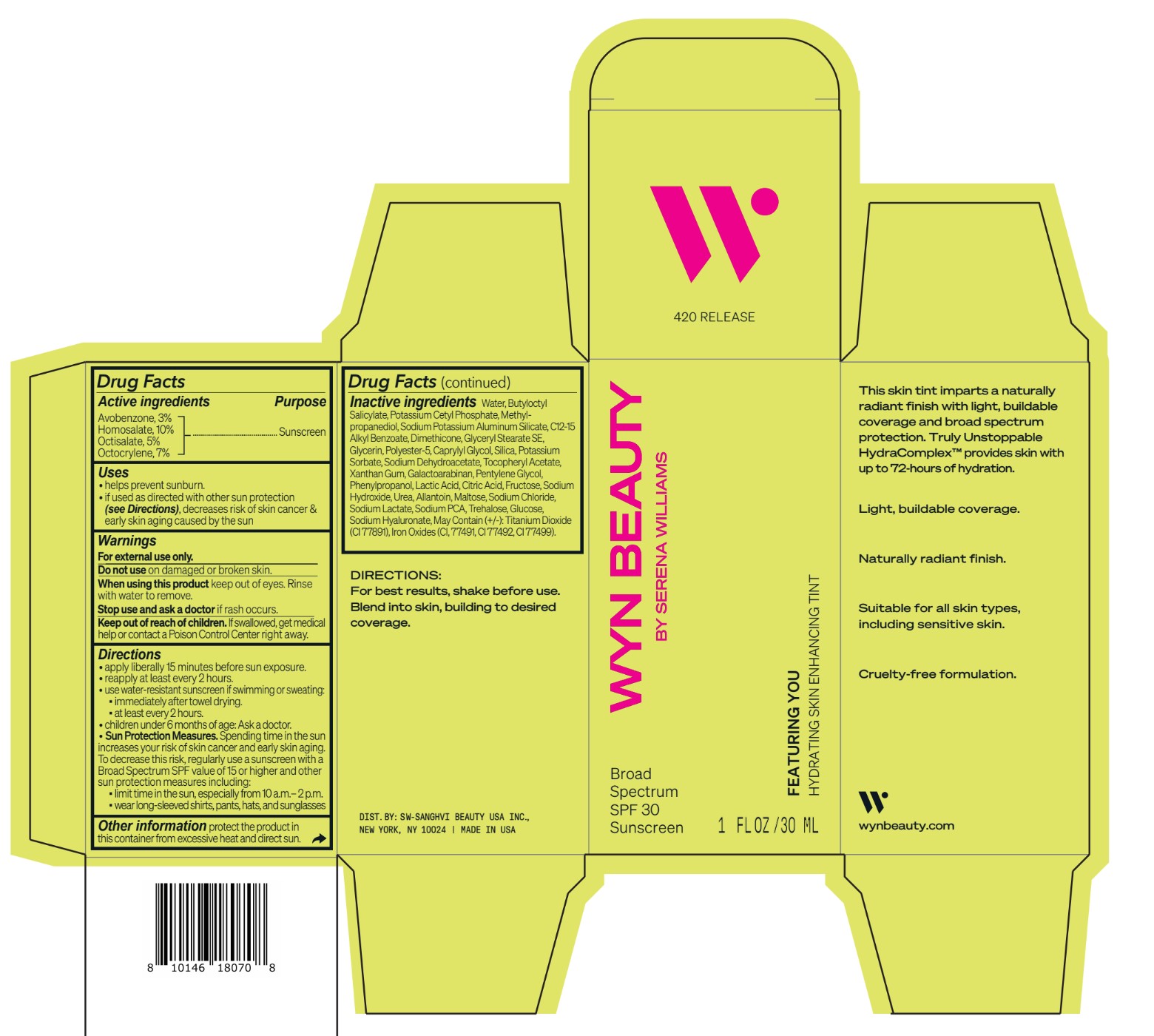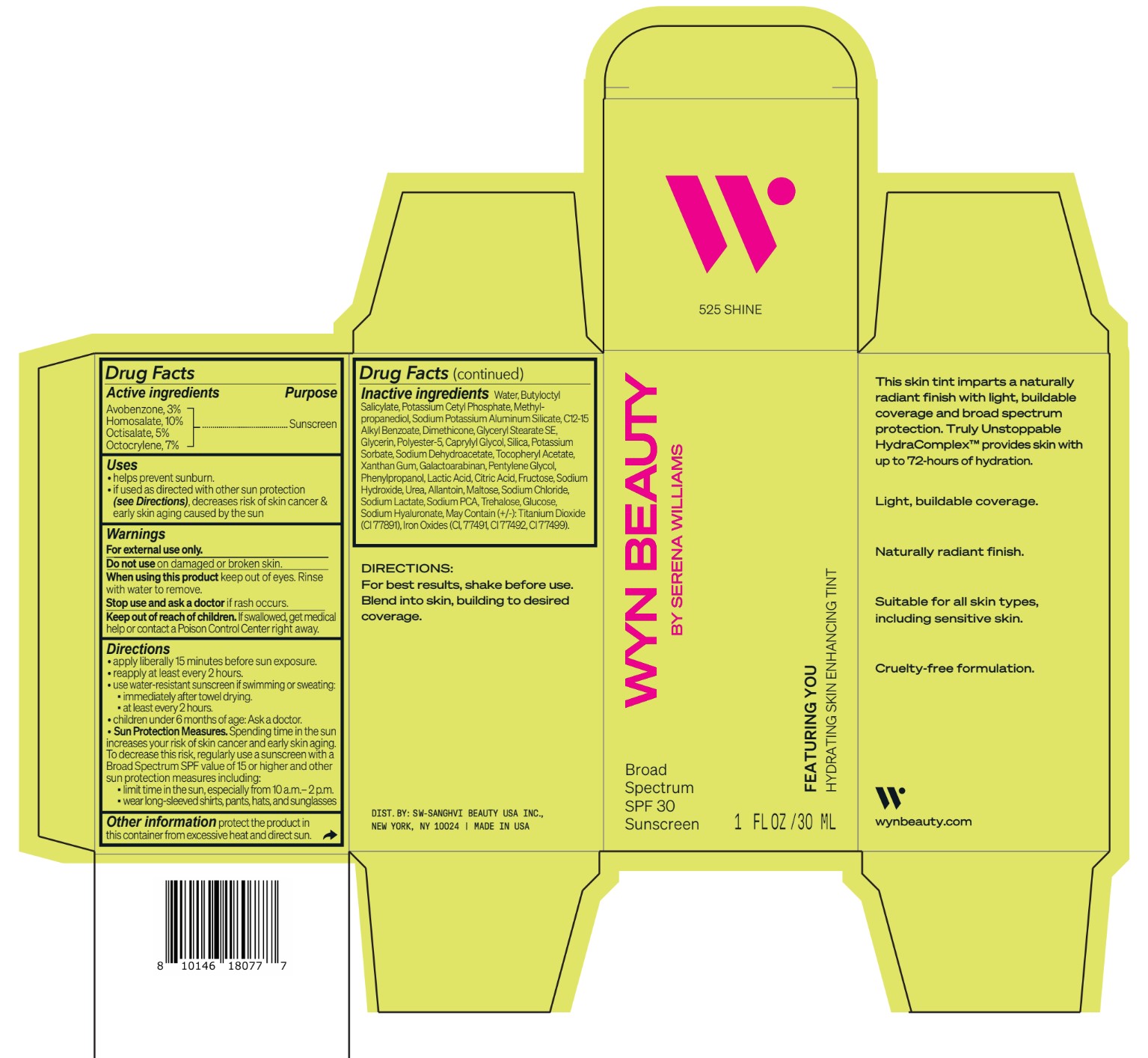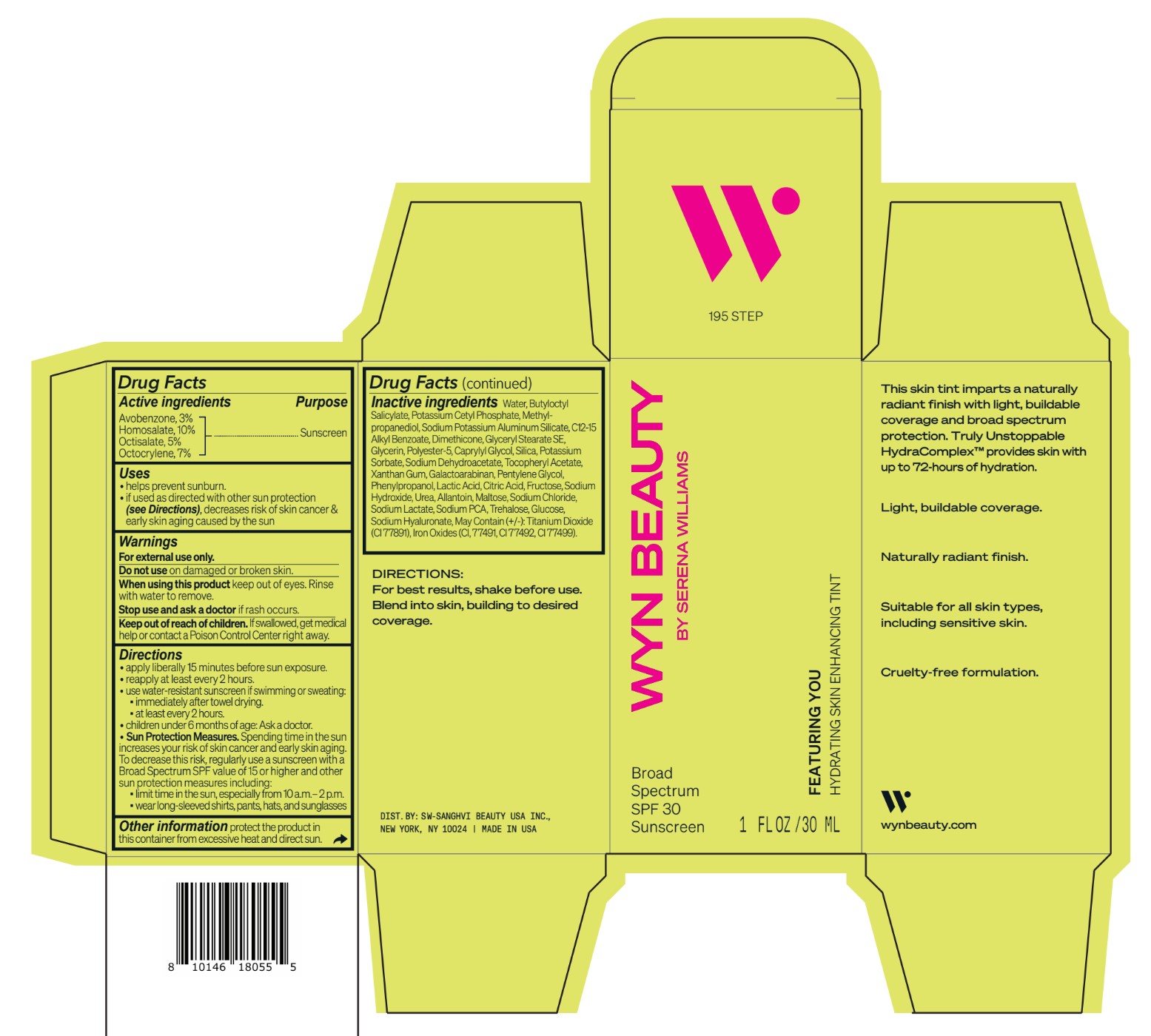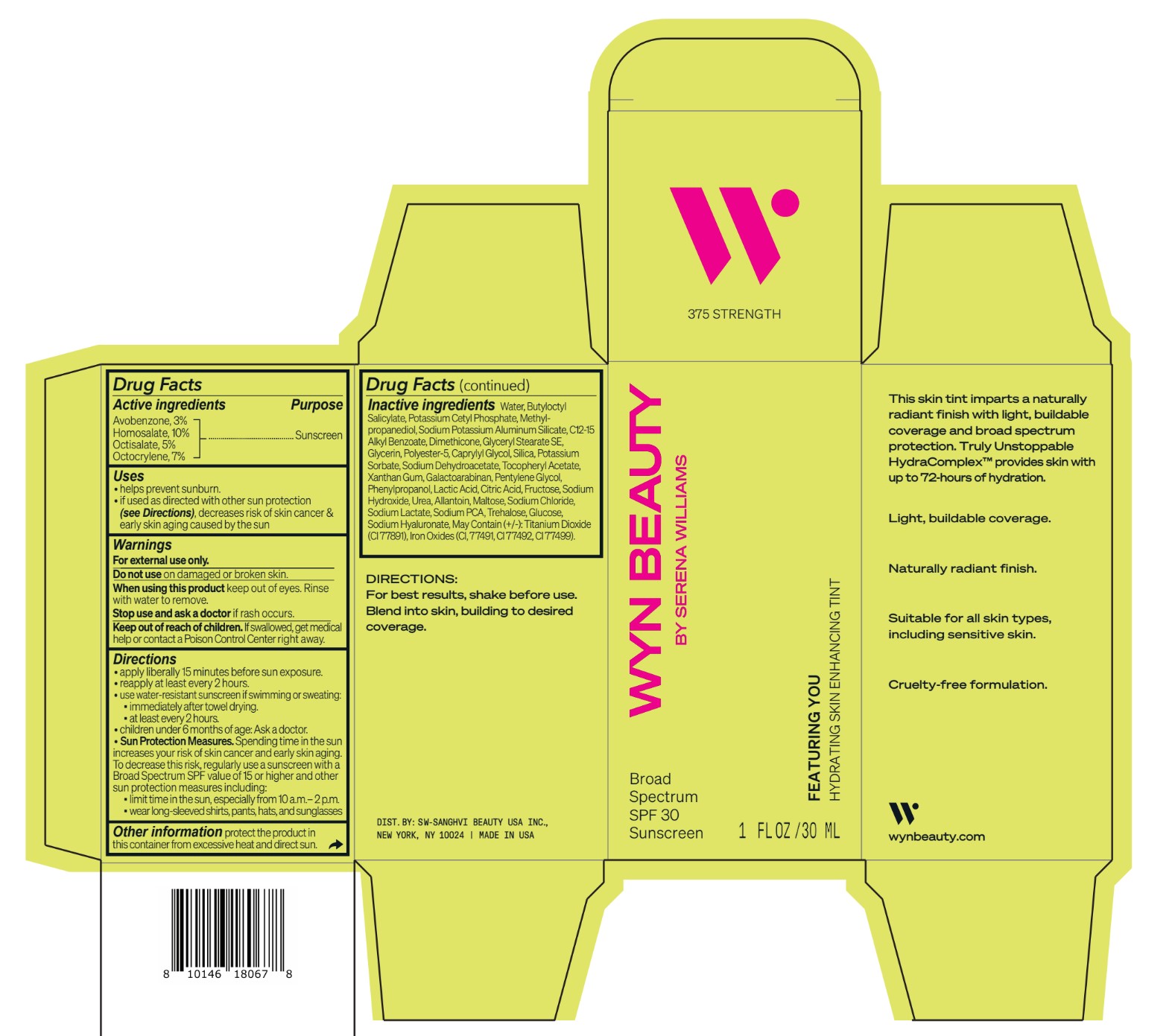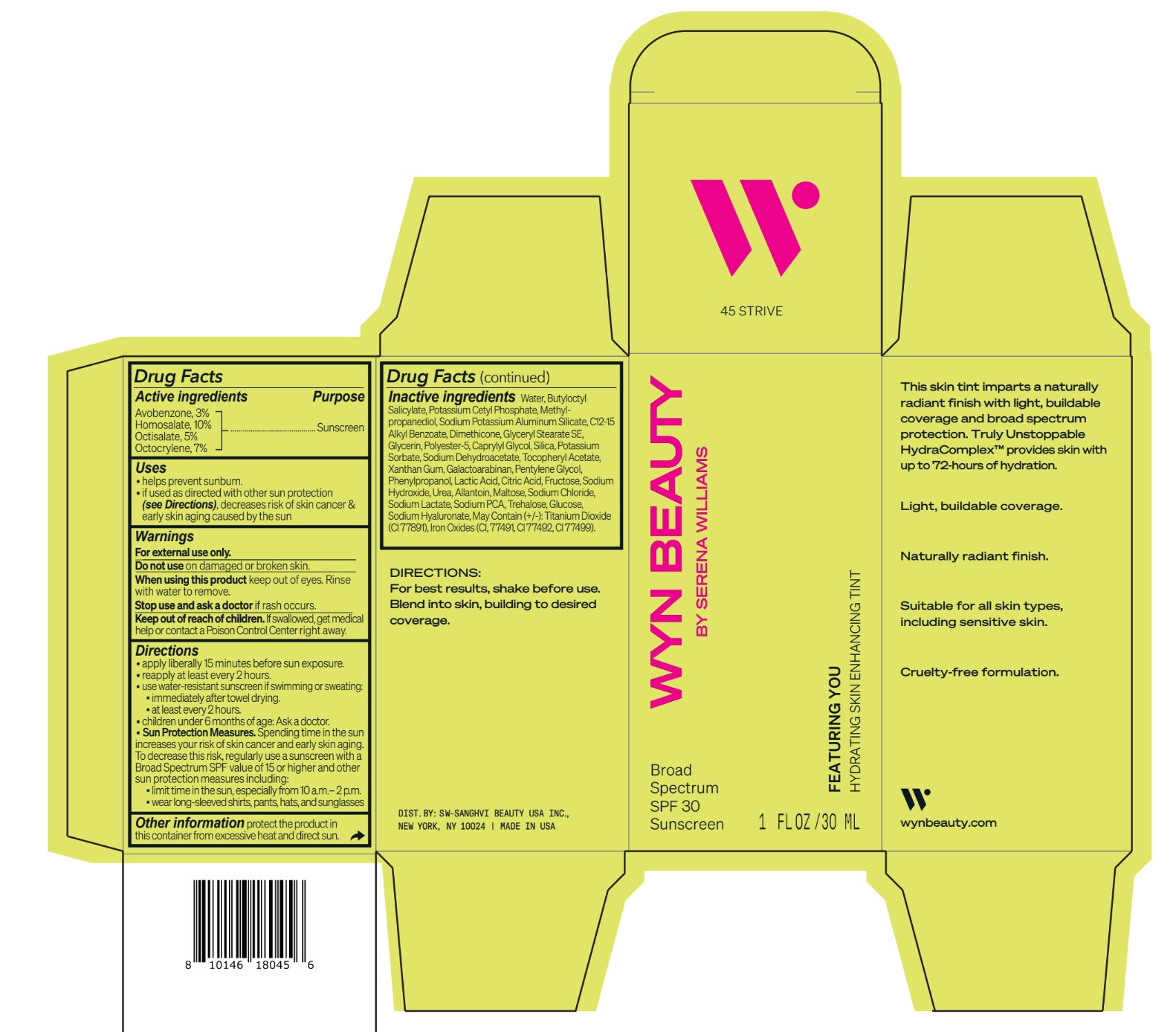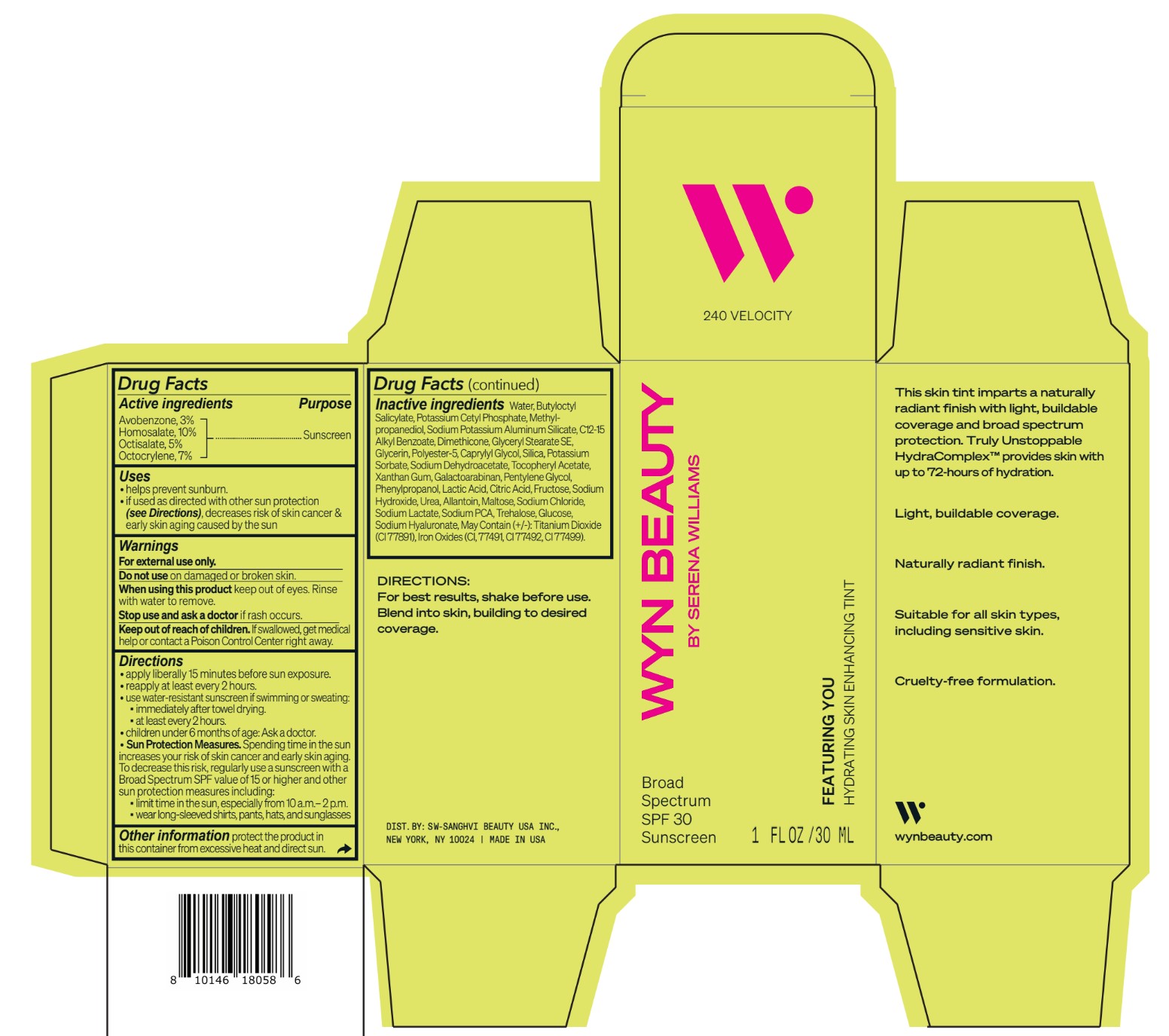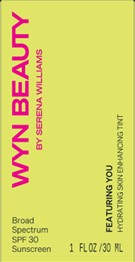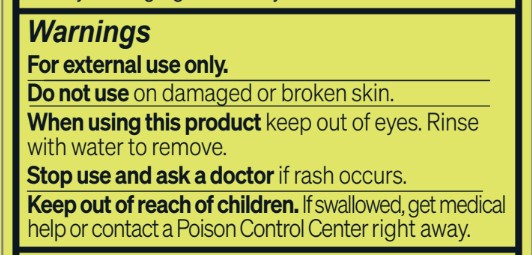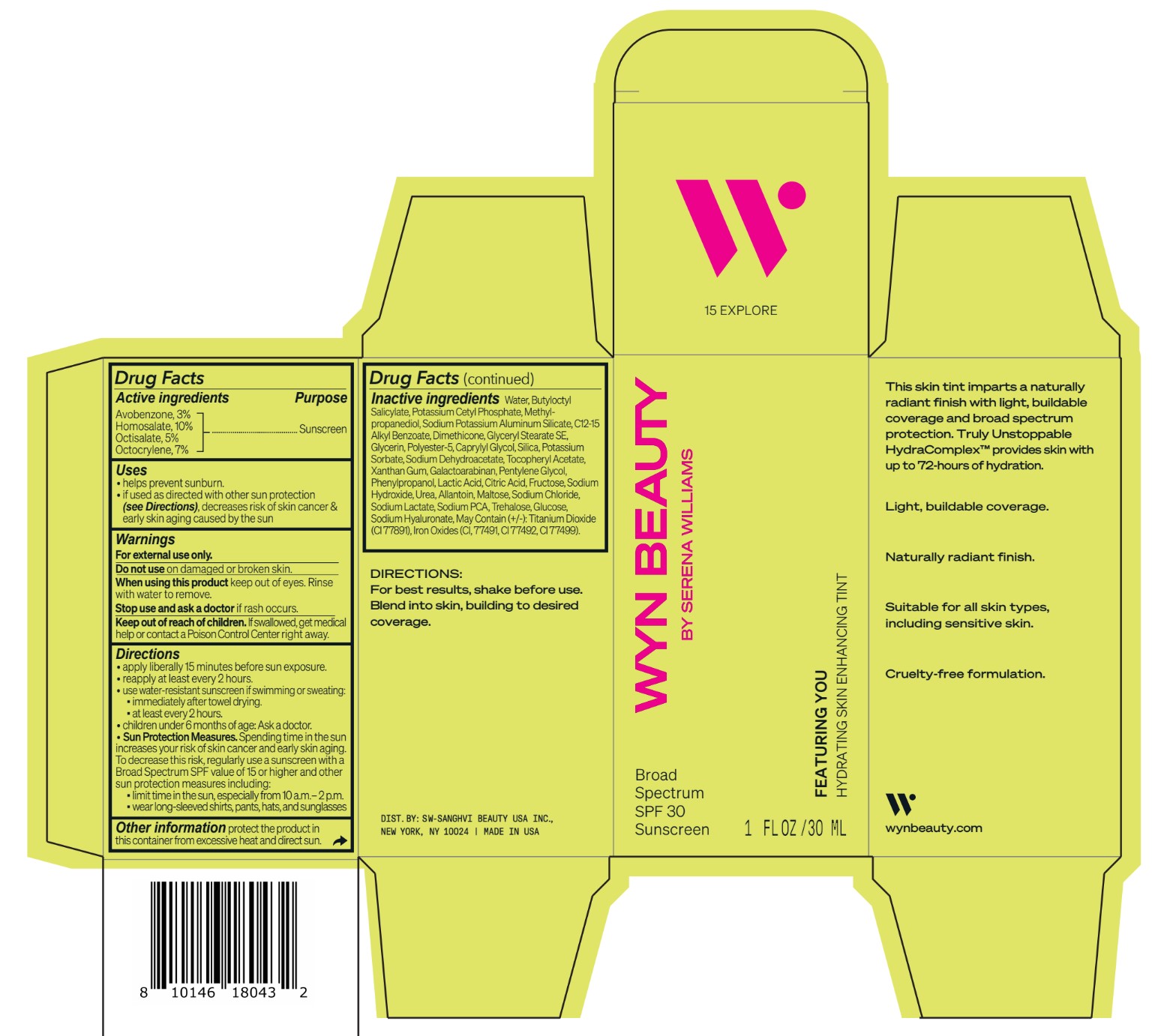 DRUG LABEL: CO-BB-54429 Featuring You Hydrating Skin Enhancing Tint SPF30-225 BECOME
NDC: 84504-3015 | Form: LOTION
Manufacturer: SW-SANGHVI BEAUTY USA, INC.
Category: otc | Type: HUMAN OTC DRUG LABEL
Date: 20240401

ACTIVE INGREDIENTS: HOMOSALATE 10 g/100 mL; OCTOCRYLENE 7 g/100 mL; OCTISALATE 5 g/100 mL; AVOBENZONE 3 g/100 mL
INACTIVE INGREDIENTS: PHENYLPROPANOL; SODIUM PYRROLIDONE CARBOXYLATE; POTASSIUM CETYL PHOSPHATE; POLYESTER-5 (TG-38); SODIUM DEHYDROACETATE; .ALPHA.-TOCOPHEROL ACETATE; PENTYLENE GLYCOL; LACTIC ACID, UNSPECIFIED FORM; ALLANTOIN; FERRIC OXIDE YELLOW; FRUCTOSE; ANHYDROUS DEXTROSE; HYALURONATE SODIUM; ALKYL (C12-15) BENZOATE; SODIUM POTASSIUM ALUMINUM SILICATE; DIMETHICONE; GLYCERYL STEARATE SE; SILICON DIOXIDE; POTASSIUM SORBATE; XANTHAN GUM; GALACTOARABINAN; CITRIC ACID MONOHYDRATE; SODIUM CHLORIDE; SODIUM LACTATE; TITANIUM DIOXIDE; FERRIC OXIDE RED; FERROSOFERRIC OXIDE; CAPRYLYL GLYCOL; SODIUM HYDROXIDE; UREA; MALTOSE ANHYDROUS; TREHALOSE; GLYCERIN; METHYLPROPANEDIOL; BUTYLOCTYL SALICYLATE; WATER

Wyn Beauty by Serena Williams - Featuring You Hydrating Skin Enhancing Tint SPF30

Directions
• apply liberally 15 minutes before sun exposure.
•reapply at least every 2 hours.
• use water-resistant sunscreen if swimming or sweating:
▪immediately after towel drying.
▪ at least every 2 hours.
• children under 6 months of age: Ask a doctor.
• Sun Protection Measures. Spending time in the sun
increases your risk of skin cancer and early skin aging.
To decrease this risk, regularly use a sunscreen with a
Broad Spectrum SPF value of 15 or higher and other
sun protection measures including:
▪limit time in the sun, especially from 10 a.m.– 2 p.m.
▪ wear long-sleeved shirts, pants, hats, and sunglasses

Uses
• helps prevent sunburn.
•if used as directed with other sun protection
(see Directions), decreases risk of skin cancer &
early skin aging caused by the sun

INACTIVE INGREDIENT

Inactive ingredients Water, Butyloctyl Salicylate, Potassium Cetyl Phosphate, Methylpropanediol, Sodium Potassium Aluminum Silicate, C12-15 Alkyl Benzoate, Dimethicone, Glyceryl Stearate SE, Glycerin, Polyester-5, Caprylyl Glycol, Silica, Potassium Sorbate, Sodium Dehydroacetate, Tocopheryl Acetate, Xanthan Gum, Galactoarabinan, Pentylene Glycol, Phenylpropanol, Lactic Acid, Citric Acid, Fructose, Sodium Hydroxide, Urea, Allantoin, Maltose, Sodium Chloride, Sodium Lactate, Sodium PCA, Trehalose, Glucose, Sodium Hyaluronate, May Contain (+/-): Titanium Dioxide (CI 77891), Iron Oxides (CI, 77491, CI 77492, CI 77499).

Keep out of reach of children. If swallowed, get medical
help or contact a Poison Control Center right away.

OTC - Purpose section
Active ingredients Purpose
Avobenzone, 3%
Homosalate, 10%
Octisalate, 5%
Octocrylene, 7%
........ Sunscreen

Warnings
For external use only.
Do not use on damaged or broken skin.
When using this product keep out of eyes. Rinse
with water to remove.
Stop use and ask a doctor if rash occurs.
Keep out of reach of children. If swallowed, get medical
help or contact a Poison Control Center right away

Featuring You Hydrating Skin Enhancing Tint SPF30

WYN BEAUTY
BY SERENA WILLIAMS
Broad
Spectrum
SPF 30
Sunscreen
FEATURING YOU
HYDRATING SKIN ENHANCING TINT
1 FL OZ / 30 ML